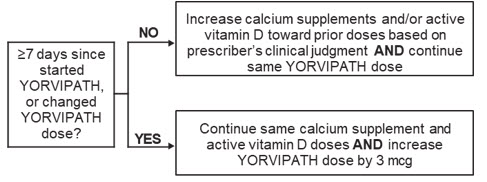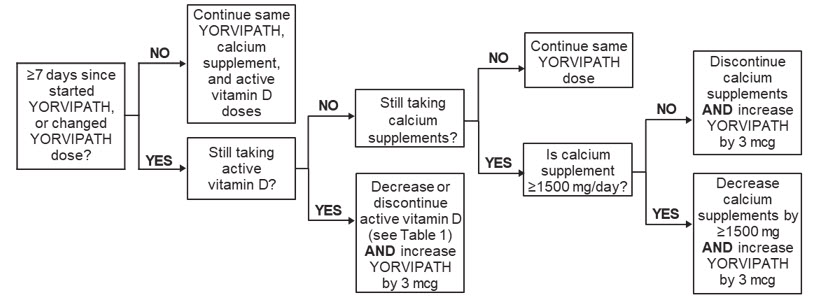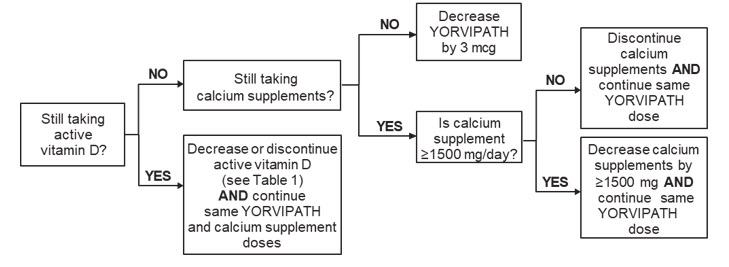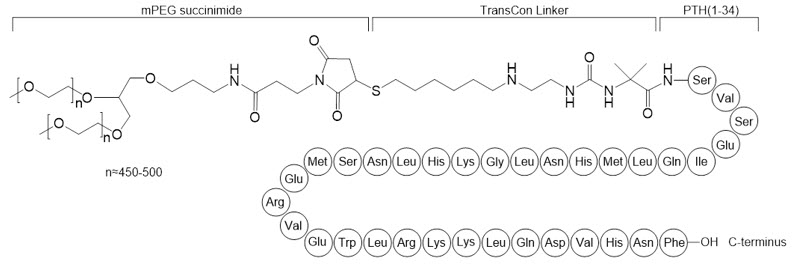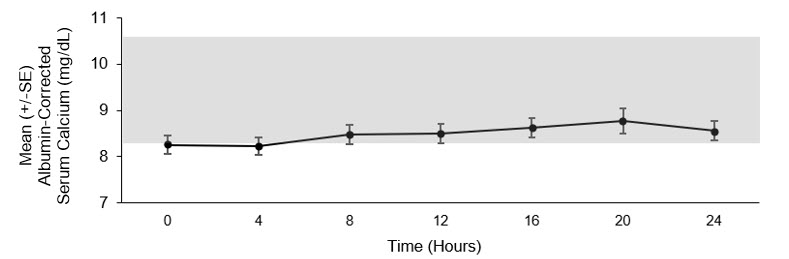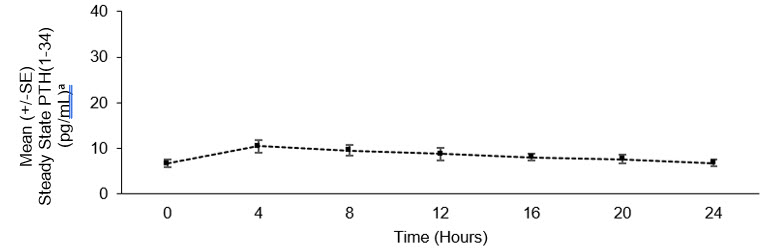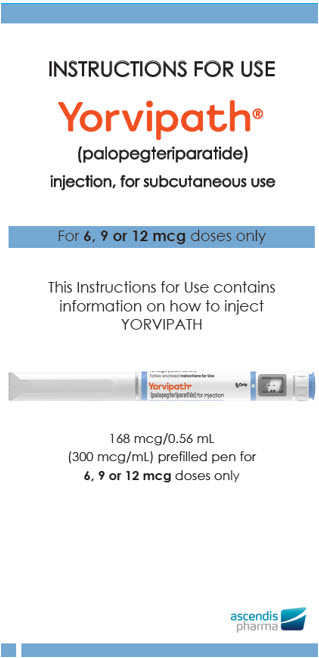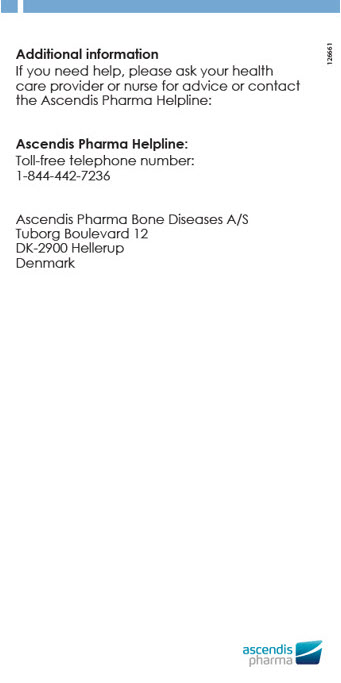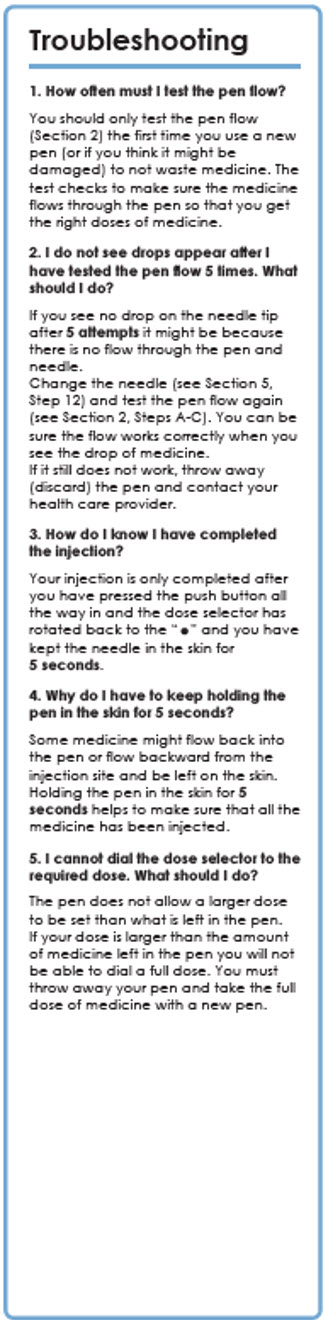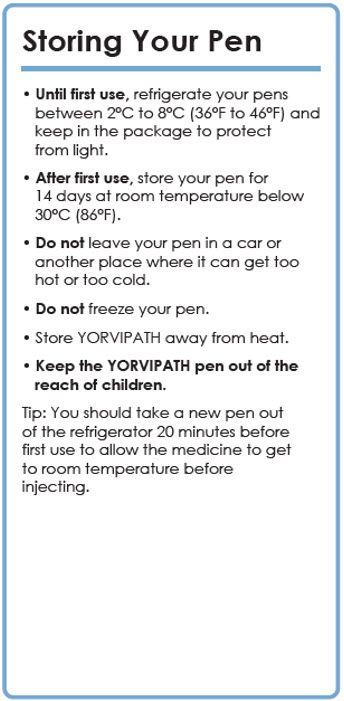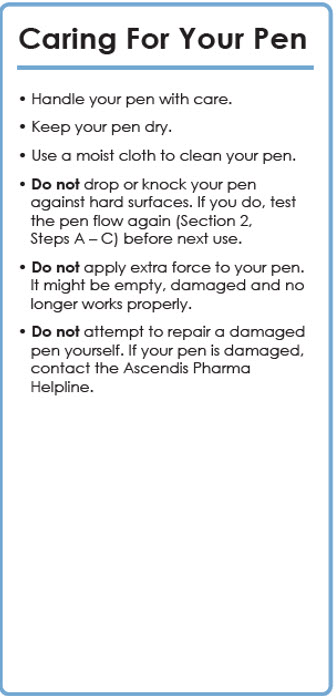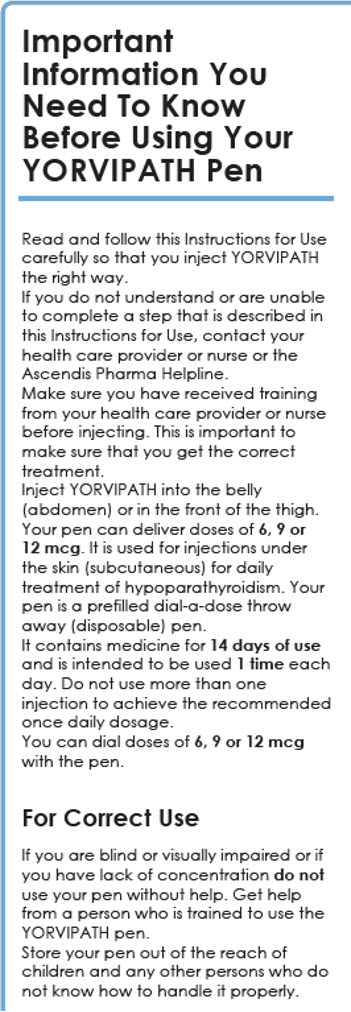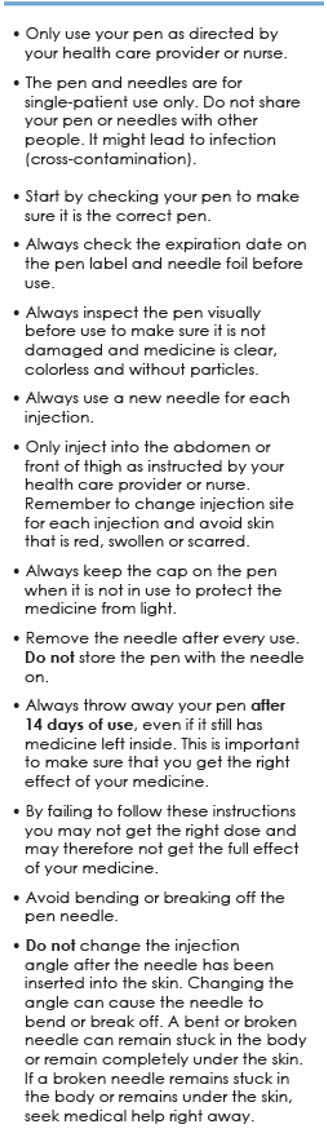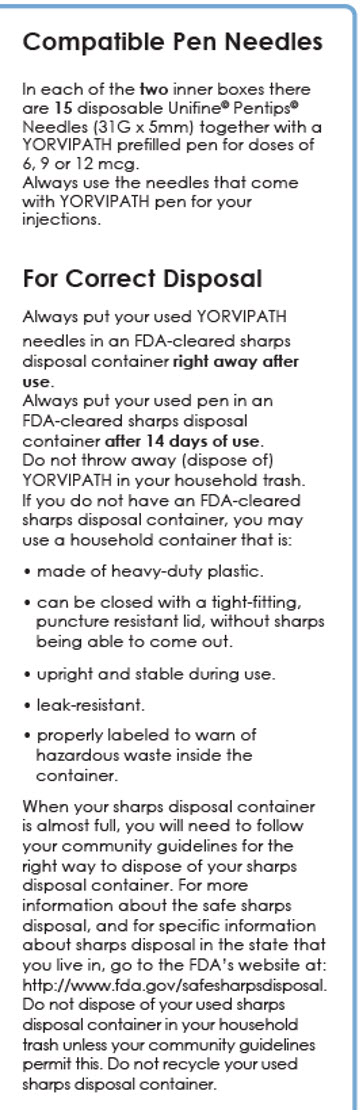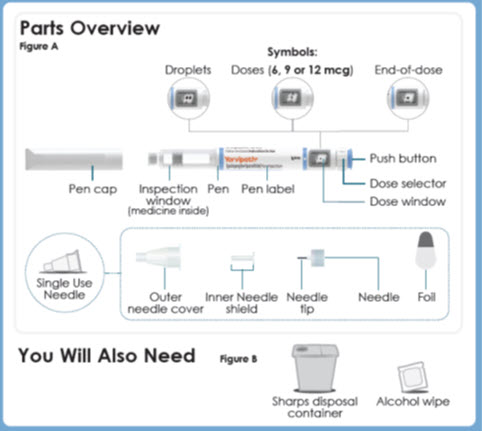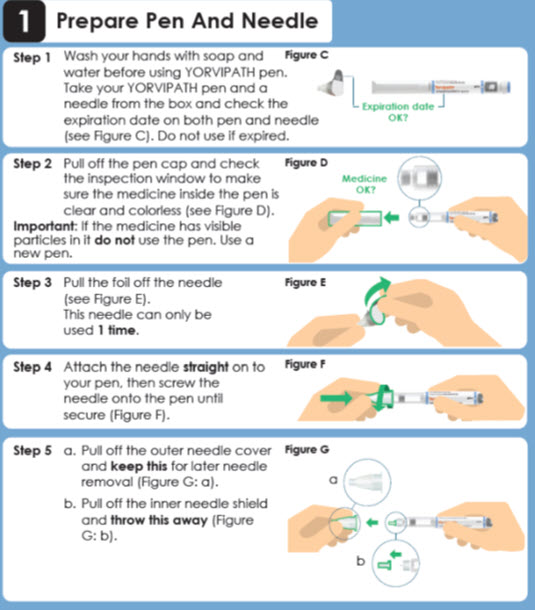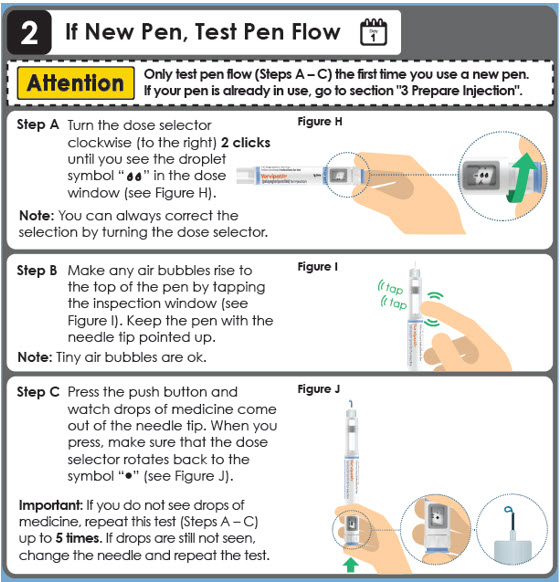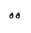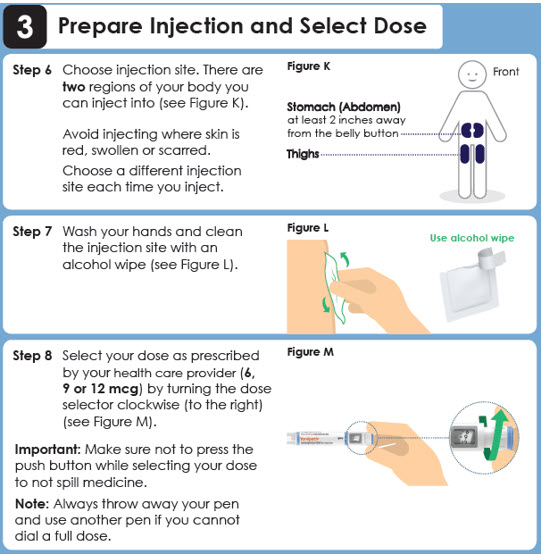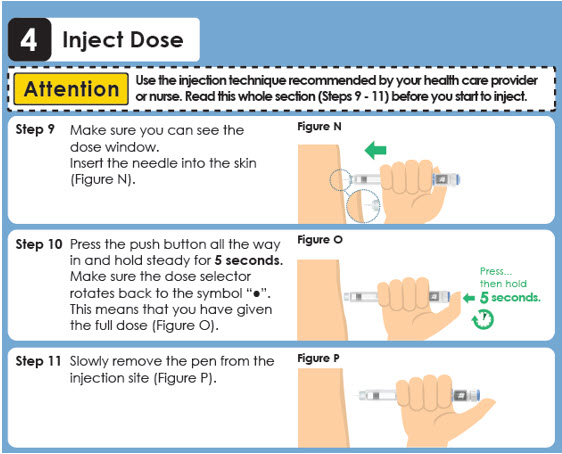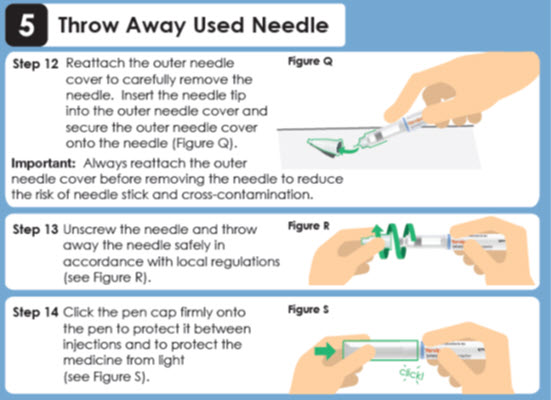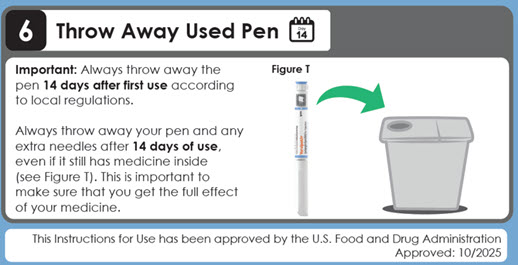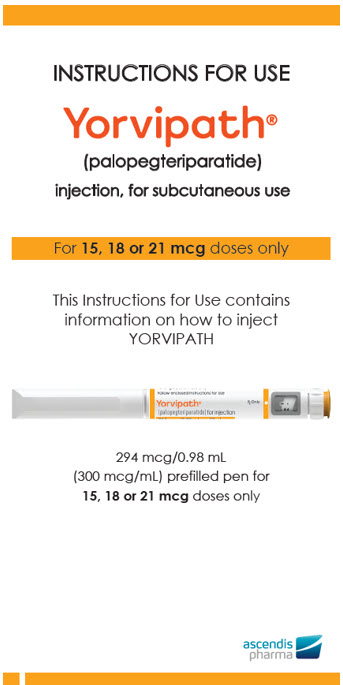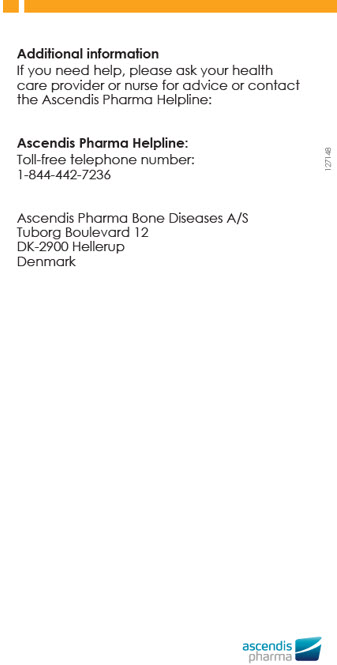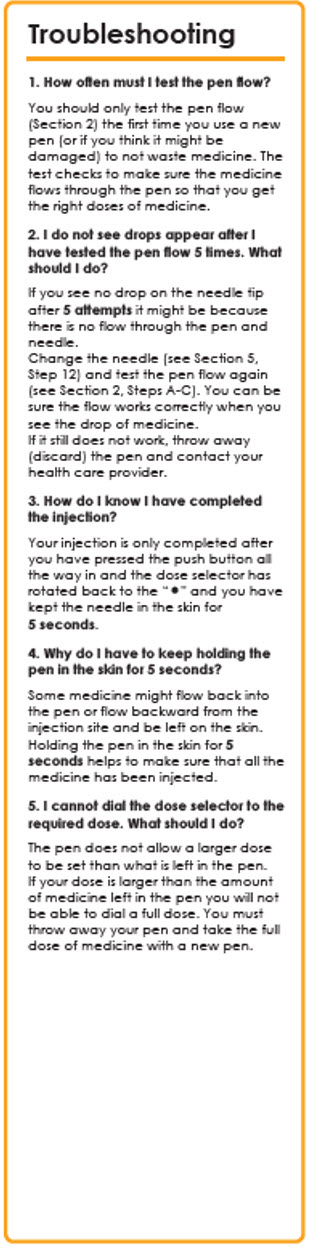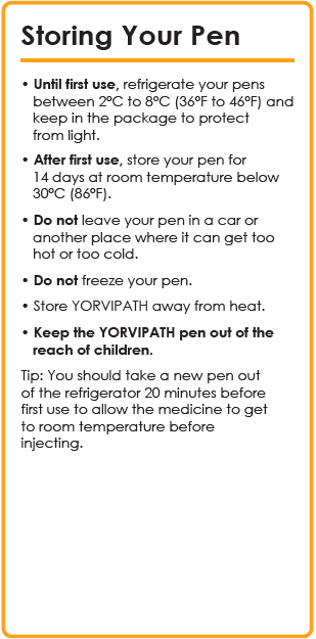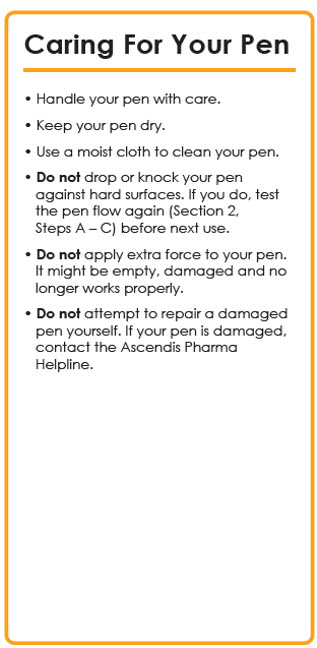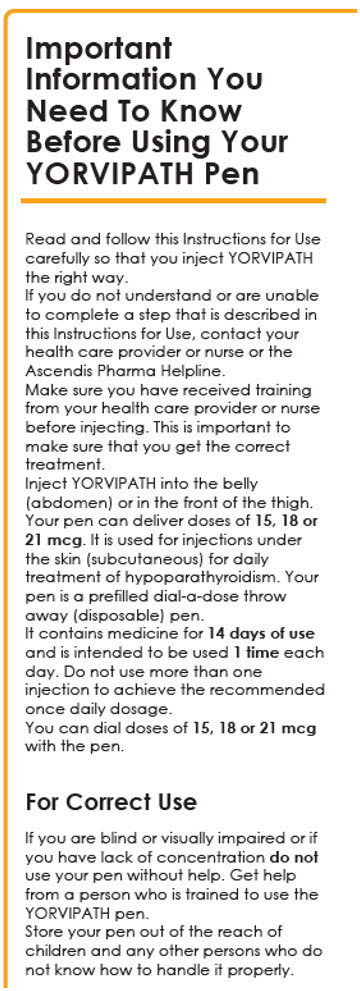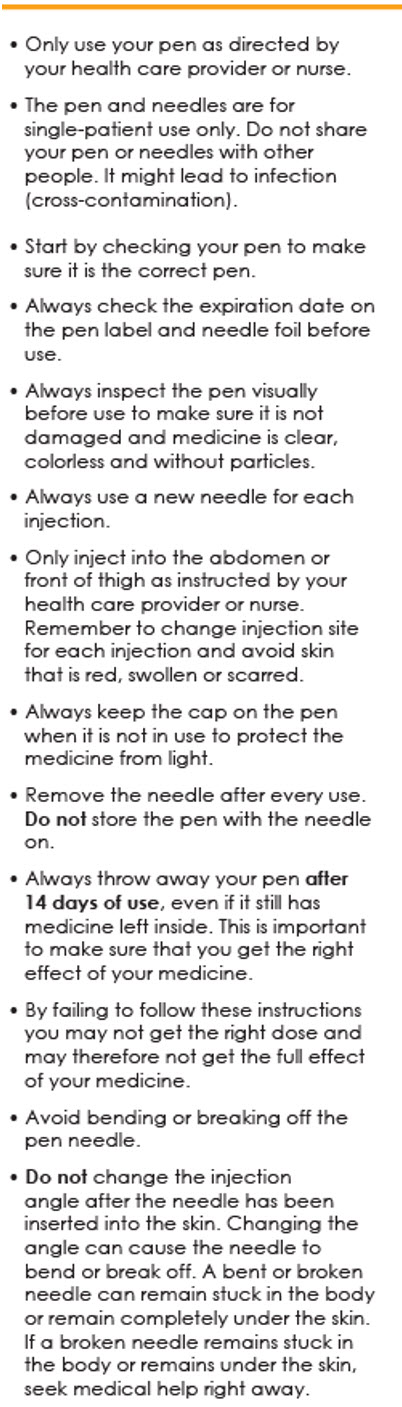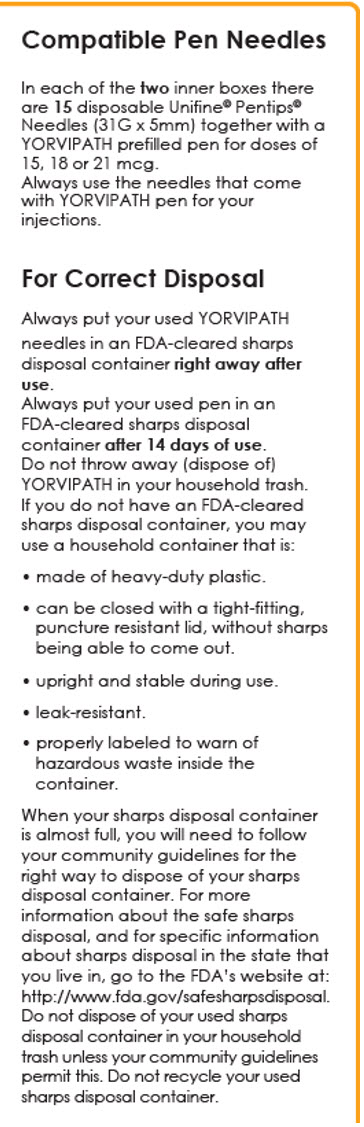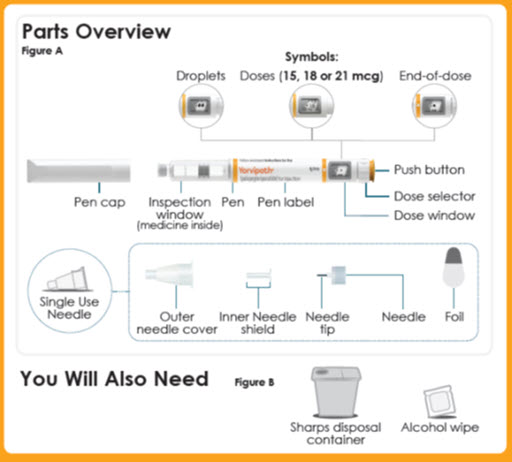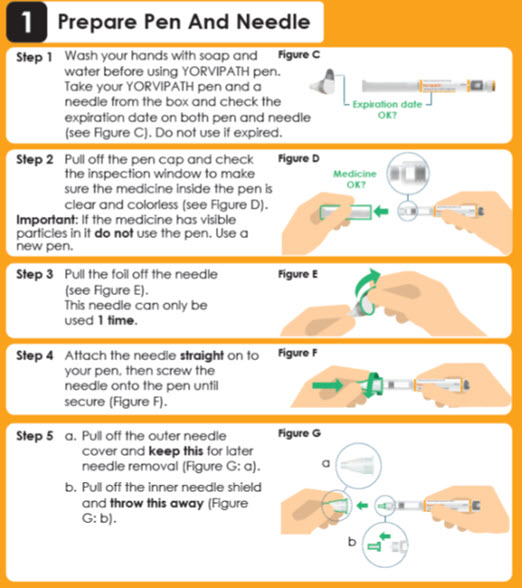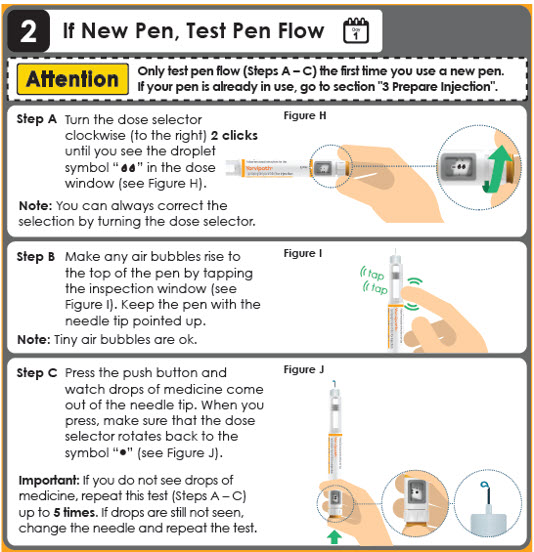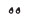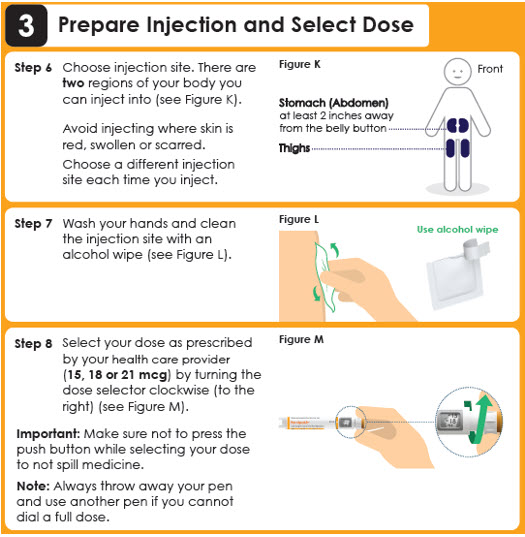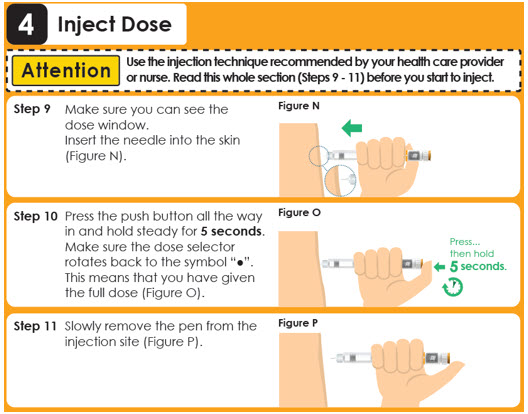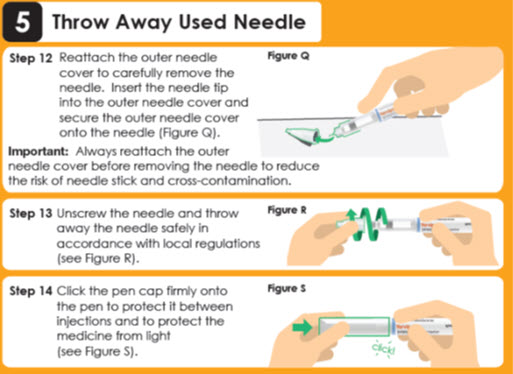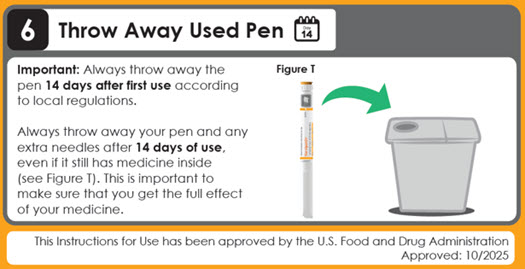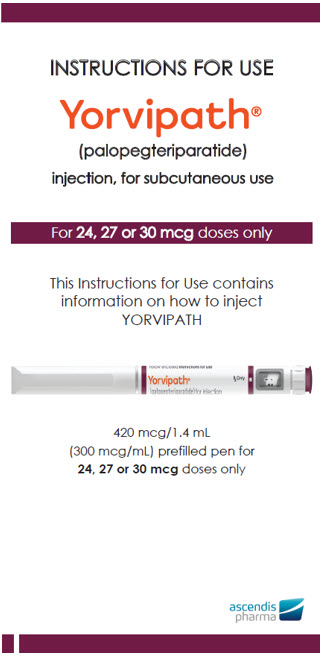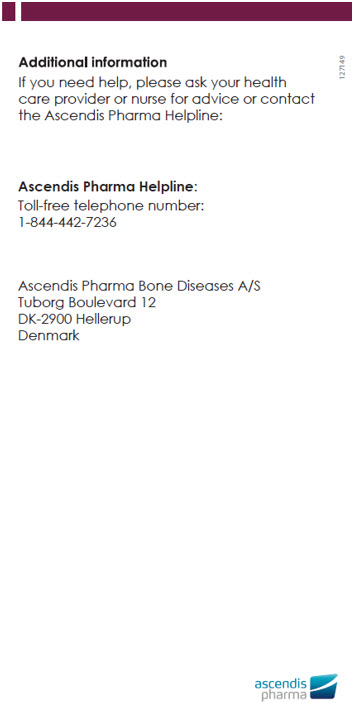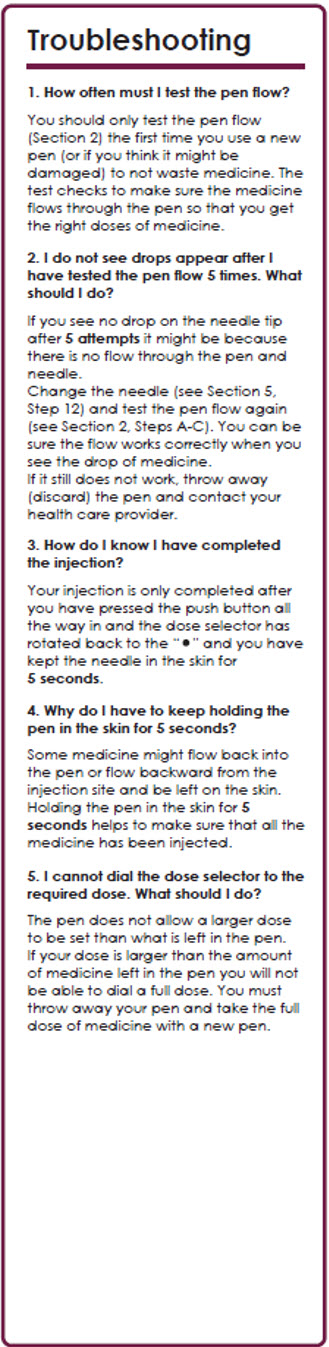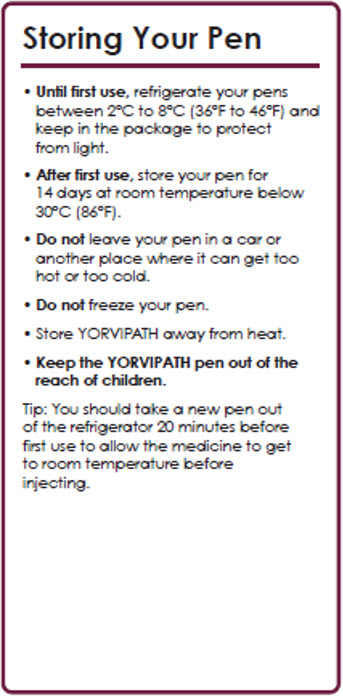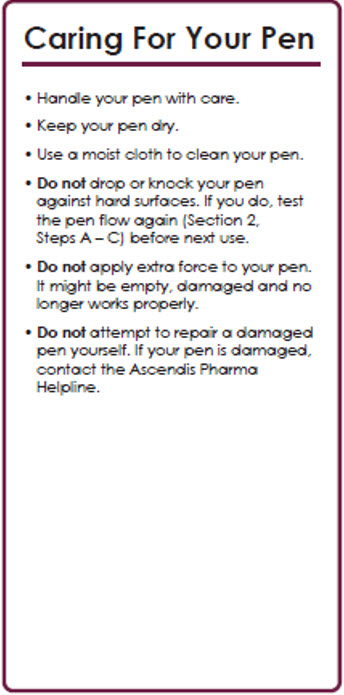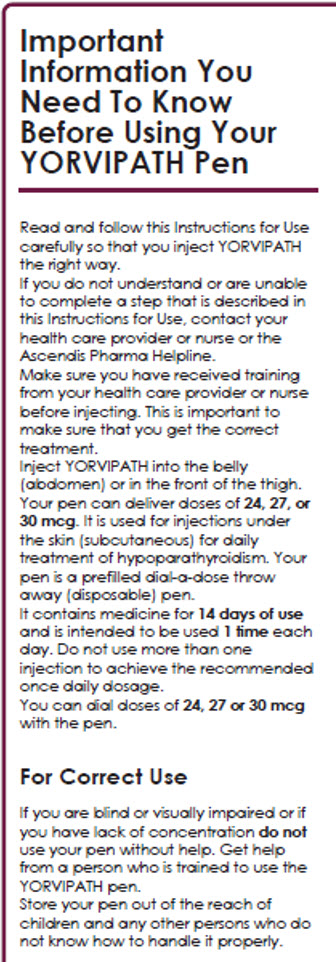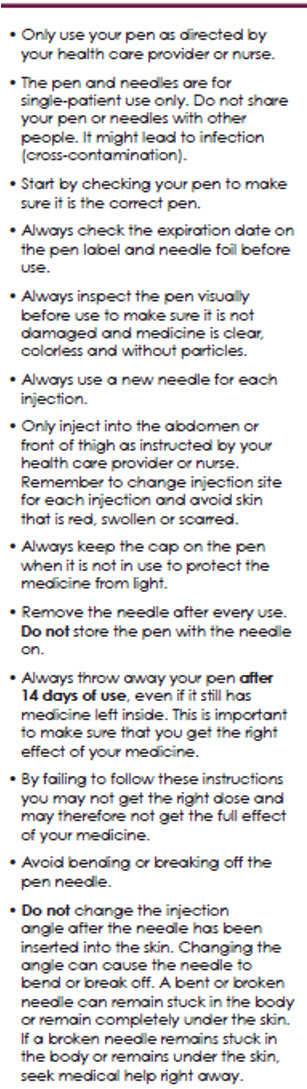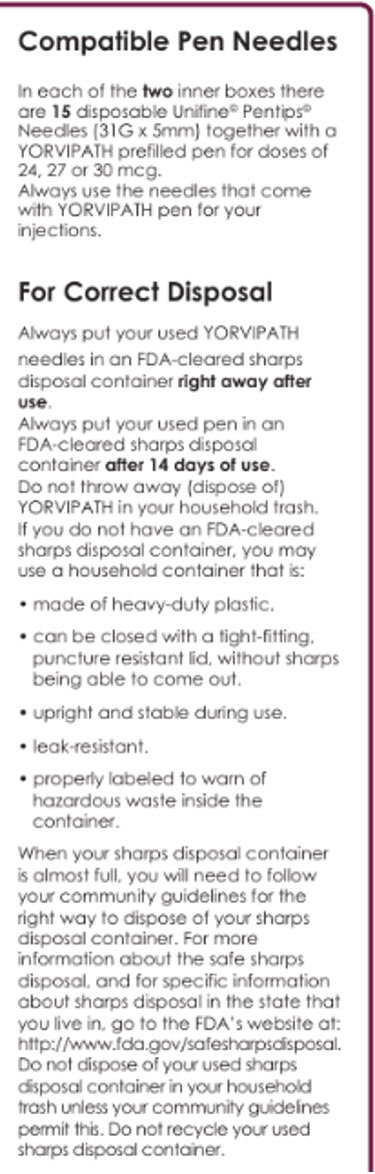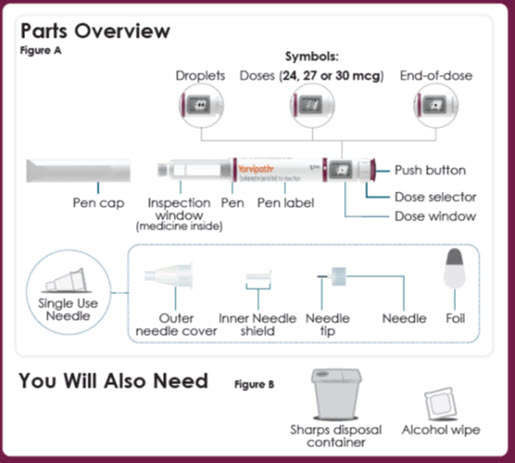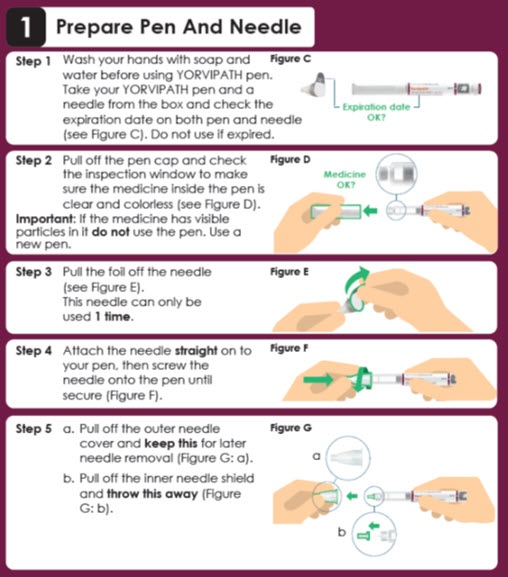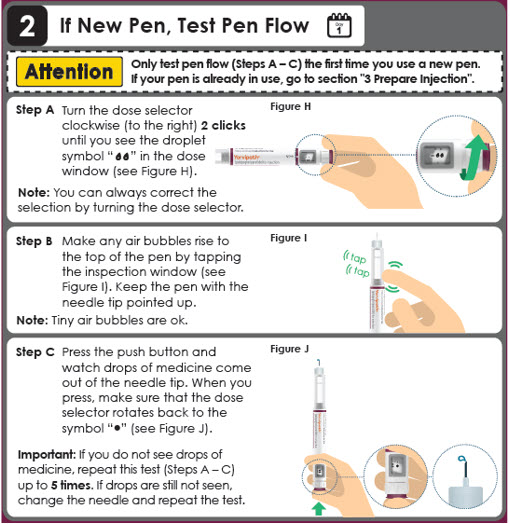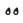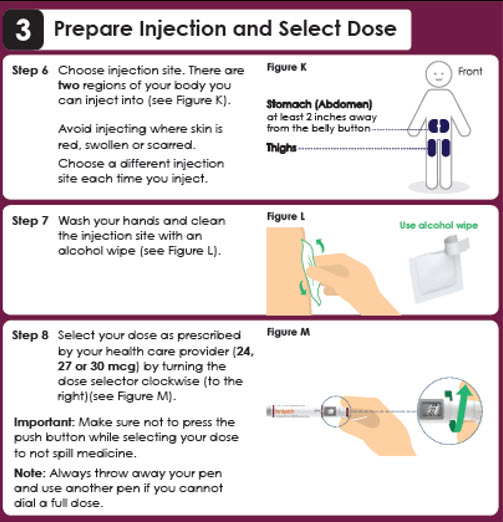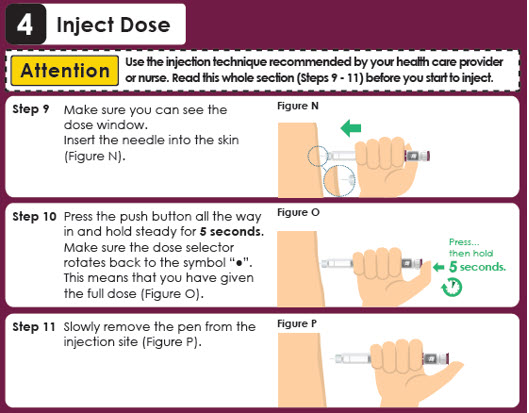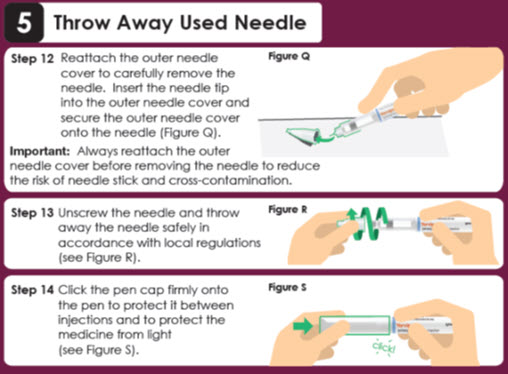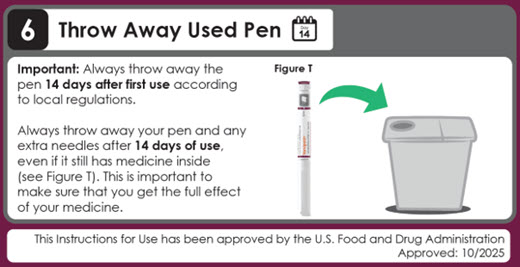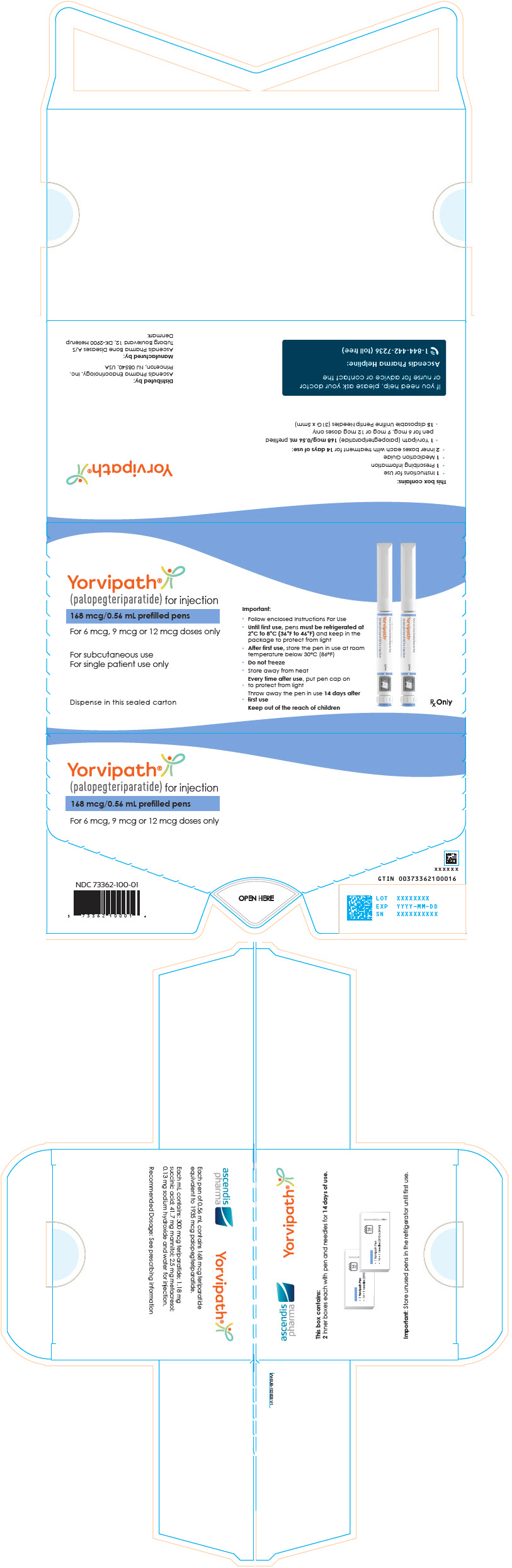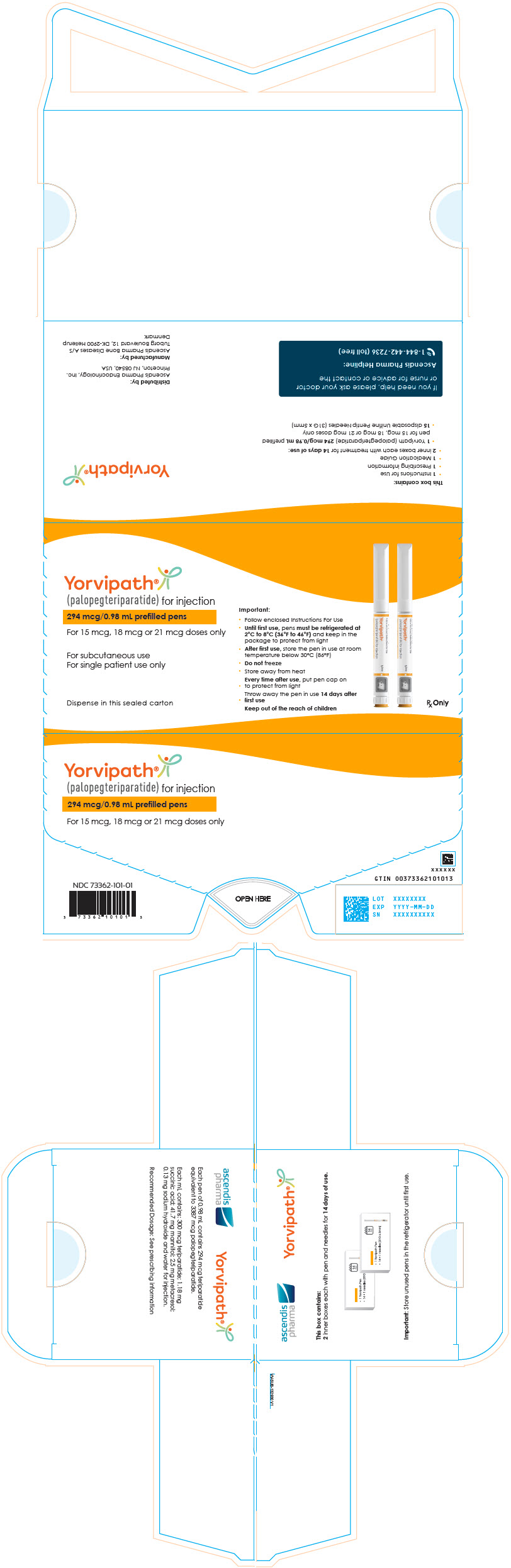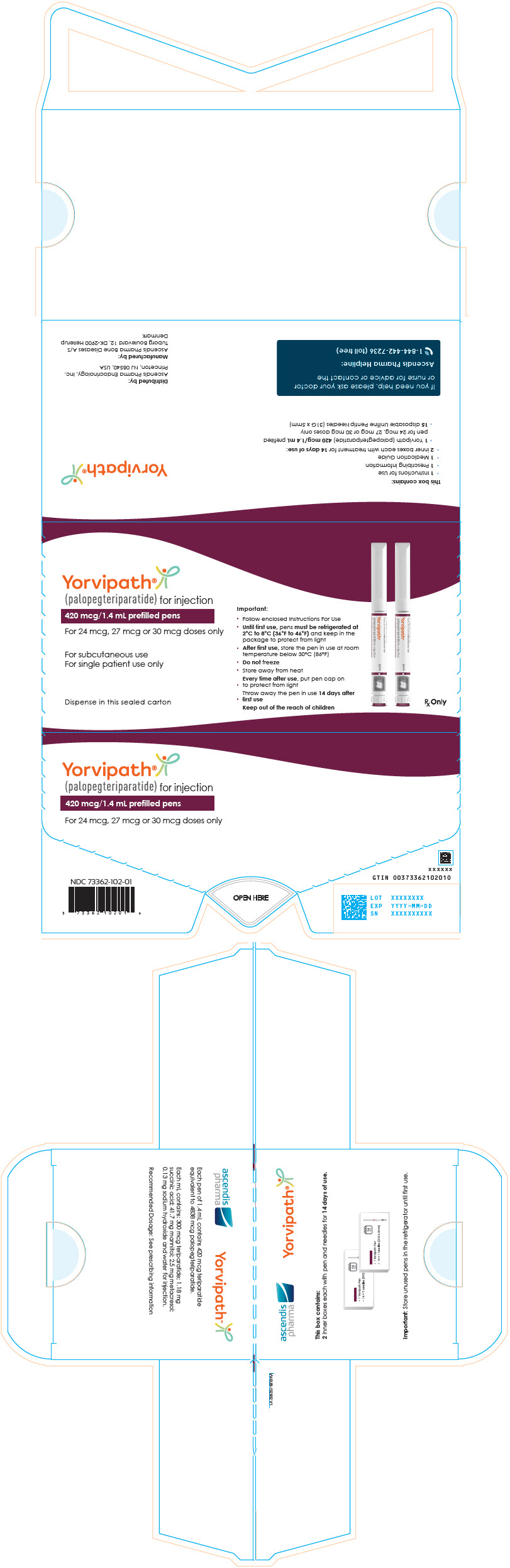 DRUG LABEL: Yorvipath
NDC: 73362-100 | Form: INJECTION, SOLUTION
Manufacturer: Ascendis Pharma, Endocrinology, Inc.
Category: prescription | Type: HUMAN PRESCRIPTION DRUG LABEL
Date: 20251027

ACTIVE INGREDIENTS: Palopegteriparatide 168 ug/0.56 mL

HIGHLIGHTS OF PRESCRIBING INFORMATION

These highlights do not include all the information needed to use YORVIPATH safely and effectively. See full prescribing information for YORVIPATH.
YORVIPATH® (palopegteriparatide) injection, for subcutaneous use
Initial U.S. Approval: 2024

1 INDICATIONS AND USAGE

YORVIPATH is a parathyroid hormone analog (PTH(1-34)) indicated for the treatment of hypoparathyroidism in adults. (1)

Limitations of Use:

- Not studied for acute post-surgical hypoparathyroidism. (1)
- Titration scheme only evaluated in adults who first achieved an albumin-corrected serum calcium of at least 7.8 mg/dL using calcium and active vitamin D treatment. (1)

2 DOSAGE AND ADMINISTRATION

- Use only one injection to achieve the once daily recommended dosage. (2.1)
- Maximum recommended YORVIPATH dosage is 30 mcg subcutaneously once daily. (2.1)
- Individualize YORVIPATH dosage based on serum calcium. (2.1)
- Refer to the Full Prescribing Information for complete dosage and administration information. (2)

3 DOSAGE FORMS AND STRENGTHS

Injection: single-patient-use prefilled pen (3)

- 168 mcg/0.56 mL pen, labeled doses of 6, 9, or 12 mcg
- 294 mcg/0.98 mL pen, labeled doses of 15, 18, or 21 mcg
- 420 mcg/1.4 mL pen, labeled doses of 24, 27, or 30 mcg

4 CONTRAINDICATIONS

Severe hypersensitivity to palopegteriparatide or any components of YORVIPATH. (4)

5 WARNINGS AND PRECAUTIONS

- Unintended Changes in Serum Calcium Levels Related to Number of Daily Injections: Use only one daily YORVIPATH injection. Using two YORVIPATH injections to achieve the recommended once daily dosage increases the variability of the total delivered dose. (5.1)
- Serious Hypercalcemia and Hypocalcemia: Have occurred with YORVIPATH. Periodically measure serum calcium and monitor for signs and symptoms of hypercalcemia and hypocalcemia. (5.2, 5.3)
- Potential Risk of Osteosarcoma: YORVIPATH is not recommended in patients at increased risk of osteosarcoma. (5.4)
- Orthostatic Hypotension: Has been reported with YORVIPATH. Monitor for signs and symptoms of orthostatic hypotension. (5.5)
- Digoxin Toxicity: Concomitant use with digoxin may predispose to digitalis toxicity if hypercalcemia develops. With concomitant use, frequently measure serum calcium and digoxin levels, and monitor for signs and symptoms of digoxin toxicity. (5.6, 7.1)

6 ADVERSE REACTIONS

Adverse reactions occurring in ≥5% of patients: injection site reactions, vasodilatory signs and symptoms, headache, diarrhea, back pain, hypercalcemia, and oropharyngeal pain. (6.1)

To report SUSPECTED ADVERSE REACTIONS, contact Ascendis Pharma at 1-844-442-7236 or FDA at 1-800-FDA-1088 or www.fda.gov/medwatch.

7 DRUG INTERACTIONS

Drugs Known to Affect Calcium: When used concomitantly with YORVIPATH, measure serum calcium levels more frequently. (7.2)

8 USE IN SPECIFIC POPULATIONS

Lactation: Monitor breastfed infants for symptoms of hypercalcemia or hypocalcemia. Consider monitoring serum calcium in the breastfed infant (8.2).

FULL PRESCRIBING INFORMATION

1 INDICATIONS AND USAGE

YORVIPATH is indicated for the treatment of hypoparathyroidism in adults.

Limitations of Use

- YORVIPATH was not studied for acute post-surgical hypoparathyroidism.
- YORVIPATH's titration scheme was only evaluated in adults who first achieved an albumin-corrected serum calcium of at least 7.8 mg/dL using calcium and active vitamin D treatment [see Dosage and Administration (2.3, 2.4) and Clinical Studies (14)].

2 DOSAGE AND ADMINISTRATION

2.1 Overview of Dosage and Monitoring

- Use only one injection to achieve the once daily recommended dosage. Using two injections to achieve the recommended once daily dosage increases the risk of unintended changes in serum calcium levels, including hypocalcemia and hypercalcemia. [see Dosage and Administration (2.4, 2.6) and Warnings and Precautions (5.1)].
- The maximum recommended dosage is 30 mcg subcutaneously once daily. If an adequate response is not achieved with a maximum YORVIPATH dosage of 30 mcg, consider adding or restarting calcium and/or active vitamin D therapy and/or seek other treatment options [see Warnings and Precautions (5.1)].
- YORVIPATH's once daily subcutaneous dosage is individualized. The recommended starting dosage is 18 mcg once daily and is titrated in 3 mcg increments or decrements with the goal of maintaining serum calcium within the normal range without the need for active vitamin D (e.g., calcitriol) or therapeutic calcium doses (elemental calcium >600 mg/day). Calcium supplementation sufficient to meet daily dietary requirements may be continued.
- Advise patients to monitor daily for clinical signs and symptoms of hypocalcemia or hypercalcemia.
- Measure serum calcium 7 to 10 days after the first YORVIPATH dose and after any dose change in YORVIPATH, active vitamin D, or calcium supplements, and monitor for clinical signs and symptoms of hypocalcemia or hypercalcemia. Once the YORVIPATH maintenance dosage is achieved, measure serum calcium levels at a minimum every 4 to 6 weeks or as indicated for symptoms of hypocalcemia or hypercalcemia.
- Adjust YORVIPATH, active vitamin D, and/or calcium supplements per Figure 1. Some patients may require an increase in the YORVIPATH dose over time to maintain the same therapeutic effect [see Clinical Studies (14)].
- Refer to the Instructions for Use (IFU) for detailed instructions on the proper preparation and administration of YORVIPATH [see Dosage and Administration (2.6)].

2.2 Laboratory Testing Prior to Initiation of YORVIPATH

- Within two weeks before the first dose of YORVIPATH, confirm serum 25(OH) vitamin D is within the normal range and albumin-corrected serum calcium is ≥7.8 mg/dL.

2.3 Modification of Active Vitamin D and Calcium Supplements on Day of YORVIPATH Initiation or Up-titration

- On the day of initiation or up-titration of YORVIPATH, adjust the dose of active vitamin D and calcium supplements based on albumin-corrected serum calcium and current active vitamin D intake (Table 1).

Table 1: Dosage Adjustments to Active Vitamin D (calcitriol) and Calcium Supplements upon Initiation or Up-titration of YORVIPATH Treatment
Albumin-Corrected Serum Calcium | Current Active Vitamin D (calcitriol) Intake | Adjust Active Vitamin D (calcitriol) Intake | Adjust Calcium Supplements
≥8.3 mg/dL | >1 mcg/day | Reduce calcitriol dosage by ≥50% | Maintain current calcium dosage
≥8.3 mg/dL | ≤1 mcg/day | Discontinue calcitriol | Maintain current calcium dosage
≥7.8 to <8.3 mg/dL | Any amount | Reduce calcitriol dosage by ≥50% | Maintain current calcium dosage
≥7.8 mg/dL | Not currently on active vitamin D | Not applicable | Reduce calcium daily dosage by at least 1500 mg or discontinue [If calcium supplements are needed to meet dietary requirements, continuing dietary calcium supplements at elemental dosages ≤600 mg/day may be considered instead of discontinuing the calcium entirely.] if current calcium daily dosage is ≤1500 mg/day

2.4 Recommended Dosage, Titration Scheme, and Monitoring

- The recommended starting dosage of YORVIPATH is 18 mcg once daily. Dosage adjustments should be made in 3 mcg increments or decrements. Do not increase the YORVIPATH dosage more often than every 7 days. Do not decrease the YORVIPATH dosage more often than every 3 days.
- The recommended dosage range of YORVIPATH is 6 to 30 mcg once daily.
- Measure serum calcium within 7 to 10 days after the first dose and any dose change in YORVIPATH, active vitamin D, or calcium supplements, and monitor for clinical symptoms of hypocalcemia or hypercalcemia. Adjust YORVIPATH, active vitamin D, and/or calcium supplements per Figure 1.
- The maintenance dosage is individualized and should be the YORVIPATH dose that achieves serum calcium within the normal range, without the need for active vitamin D or therapeutic doses of calcium. Calcium supplementation sufficient to meet daily dietary requirements may be continued. Once the maintenance dosage is achieved, monitor for clinical signs and symptoms of hypocalcemia or hypercalcemia and measure serum calcium levels as indicated, and at a minimum every 4 to 6 weeks, as some patients may require further dose titration. If calcium levels remain low with the maximum recommended dosage of 30 mcg once daily, consider adding or restarting calcium and/or active vitamin D therapy and/or seek other treatment.

Titration Recommendations for Albumin-Corrected Serum Calcium Less Than 12 mg/dL

Figure 1 shows dosage titration recommendations for YORVIPATH, active vitamin D, and calcium in adults with specific albumin-corrected serum calcium ranges that are less than or equal to 12 mg/dL. The maximum recommended dosage of YORVIPATH is 30 mcg once daily [see Dosage and Administration (2.1)].

Figure 1: Titration of YORVIPATH, Active Vitamin D, and Calcium Supplements

Albumin-Corrected Serum Calcium <8.3 mg/dL:

Albumin-Corrected Serum Calcium 8.3 to 10.6 mg/dL:

Albumin-Corrected Serum Calcium 10.7 to 11.9 mg/dL:

Titration Recommendations for Albumin-Corrected Serum Calcium 12 mg/dL or Greater

Withhold YORVIPATH for 2 to 3 days and then recheck serum calcium. If albumin-corrected serum calcium remains ≥12 mg/dL, withhold YORVIPATH for an additional 2 to 3 days and then recheck serum calcium. Once the albumin-corrected serum calcium is <12 mg/dL, resume titration of YORVIPATH, active vitamin D, and calcium supplements per the applicable section of Figure 1 using the most recent serum calcium value.

2.5 Dose Delay, Interruption, or Discontinuation of YORVIPATH

Take YORVIPATH as soon as possible if a dose is missed by less than 12 hours. Skip the missed dose if the dose has been missed by more than 12 hours. Take the next dose as scheduled.

If YORVIPATH treatment is delayed or interrupted for 3 days or more, evaluate patients for signs and symptoms of hypocalcemia and consider measuring serum calcium. If indicated, resume treatment with, or increase the dose of, calcium supplements and active vitamin D. Resume YORVIPATH at the previously prescribed dose as soon as possible after an interruption then measure serum calcium within 7 to 10 days and adjust doses of YORVIPATH, active vitamin D, and/or calcium supplements per Figure 1 [see Dosage and Administration (2.4)].

2.6 Preparation of Pen and Administration Instructions

Patients and caregivers who will administer YORVIPATH should receive appropriate training by a healthcare professional prior to first use.

Follow the Instructions For Use to administer YORVIPATH using pen and needle:

- YORVIPATH must be refrigerated at 2°C to 8°C (36°F to 46°F) until first use.
- YORVIPATH should be inspected visually for particulate matter and discoloration prior to administration, whenever solution and container permit. YORVIPATH is a clear, colorless solution. Do not use if solid particles appear or if the solution is cloudy or colored.
- When a pen is used for the first time, test pen flow.
- Click the needle straight onto the pen, then screw the needle onto the pen until secure.
- Administer YORVIPATH subcutaneously to the abdomen or front of the thigh. Rotate the injection site daily.
- YORVIPATH should be administered initially when the patient can sit or lie down because of the potential of orthostatic hypotension [see Warnings and Precautions (5.5)].

3 DOSAGE FORMS AND STRENGTHS

Injection: Clear, colorless solution in single-patient-use prefilled pens in three presentations

Table 2 displays the YORVIPATH prefilled pen presentations, strengths, labeled doses, and deliverable dose ranges.

Table 2: YORVIPATH Prefilled Pen Presentations, Strengths, Labeled Doses, and Deliverable Dose Ranges
Pen Type and Strength | Labeled Dose (mcg) | Range of Deliverable Dose [Deliverable dose range at each labeled dose setting based on prefilled pen performance. Use only labeled dose for titration (refer to Figure 1).] (Minimum – Maximum) (mcg)
Prefilled pen with blue push button (168 mcg/0.56 mL) | 6 | 4.5 - 7.5
Prefilled pen with blue push button (168 mcg/0.56 mL) | 9 | 7.5 - 10.5
Prefilled pen with blue push button (168 mcg/0.56 mL) | 12 | 10.5 - 13.5
Prefilled pen with orange push button (294 mcg/0.98 mL) | 15 | 13.1 - 16.5
Prefilled pen with orange push button (294 mcg/0.98 mL) | 18 | 16.1 - 19.5
Prefilled pen with orange push button (294 mcg/0.98 mL) | 21 | 19.1 - 22.5
Prefilled pen with burgundy push button (420 mcg/1.4 mL) | 24 | 21.6 - 25.5
Prefilled pen with burgundy push button (420 mcg/1.4 mL) | 27 | 24.6 - 28.5
 | 30 | 27.6 - 31.5

4 CONTRAINDICATIONS

YORVIPATH is contraindicated in patients with severe hypersensitivity to palopegteriparatide or to any of its excipients. Hypersensitivity reactions, including anaphylaxis, angioedema, and urticaria, have been observed with parathyroid hormone (PTH) analogs.

5 WARNINGS AND PRECAUTIONS

5.1 Risk of Unintended Changes in Serum Calcium Levels Related to Number of Daily Injections

Use only one YORVIPATH injection to achieve the recommended once daily dosage. Using two YORVIPATH injections to achieve the recommended once daily dosage increases the variability of the total delivered dose, which can cause unintended changes in serum calcium levels, including hypercalcemia and hypocalcemia [see Dosage and Administration (2.1) and Warning and Precautions (5.2, 5.3)].

5.2 Serious Hypercalcemia

Serious events of hypercalcemia requiring hospitalization have been reported with YORVIPATH. The risk is highest when starting or increasing the dose of YORVIPATH but may occur at any time. Measure serum calcium 7 to 10 days after any dose change or if there are signs or symptoms of hypercalcemia, and at a minimum of every 4 to 6 weeks once the maintenance dose is achieved. Treat hypercalcemia if needed. If albumin-corrected serum calcium is greater than 12 mg/dL, withhold YORVIPATH for at least 2-3 days [see Dosage and Administration (2.4)]. For less serious hypercalcemia, adjust the dose of YORVIPATH, active vitamin D, and/or calcium supplements [see Dosage and Administration (2), Adverse Reactions (6.1)].

5.3 Serious Hypocalcemia

Serious events of hypocalcemia have been observed with PTH products, including YORVIPATH. The risk is highest when YORVIPATH is abruptly discontinued, but may occur at any time, even in patients who have been on stable doses of YORVIPATH. Measure serum calcium 7 to 10 days after any dose change or if there are signs or symptoms of hypocalcemia, and at a minimum of every 4 to 6 weeks once the maintenance dosage is achieved. Treat hypocalcemia if needed, and adjust the dose of YORVIPATH, active vitamin D, and/or calcium supplements if hypocalcemia occurs [see Dosage and Administration (2.4)].

5.4 Potential Risk of Osteosarcoma

YORVIPATH is a PTH analog. An increased incidence of osteosarcoma (a malignant bone tumor) has been reported in male and female rats treated with PTH analogs, including teriparatide. Osteosarcoma occurrence in rats is dependent on teriparatide or PTH dose and treatment duration. Osteosarcoma has been reported in patients treated with teriparatide in the postmarketing setting; however, an increased risk of osteosarcoma has not been observed in observational studies in humans. There are limited data assessing the risk of osteosarcoma beyond 2 years of teriparatide use.

YORVIPATH is not recommended in patients who are at increased risk of osteosarcoma, such as patients with:

- Open epiphyses. YORVIPATH is not approved in pediatric patients [see Use in Specific Populations (8.4)].
- Metabolic bone diseases other than hypoparathyroidism, including Paget's disease of bone.
- Unexplained elevations of alkaline phosphatase.
- Bone metastases or a history of skeletal malignancies.
- History of external beam or implant radiation therapy involving the skeleton.
- Hereditary disorders predisposing to osteosarcoma.

Instruct patients to promptly report clinical symptoms (e.g., persistent localized pain) and signs (e.g., soft tissue mass tender to palpation) that could be consistent with osteosarcoma.

5.5 Orthostatic Hypotension

Orthostatic hypotension has been reported with YORVIPATH. Associated signs and symptoms may include decreased blood pressure, dizziness (including postural dizziness), palpitations, tachycardia, presyncope, or syncope. Such symptoms can be managed by dosing at bedtime, while reclining. YORVIPATH should be administered initially when the patient can sit or lie down due to the potential of orthostatic hypotension.

5.6 Risk of Digoxin Toxicity with Concomitant Use of Digitalis Compounds

YORVIPATH increases serum calcium, and therefore, concomitant use with digoxin (which has a narrow therapeutic index) may predispose patients to digitalis toxicity if hypercalcemia develops. Digoxin efficacy may be reduced if hypocalcemia is present. When YORVIPATH is used concomitantly with digoxin, measure serum calcium and digoxin levels routinely, and monitor for signs and symptoms of digoxin toxicity. Refer to the digoxin prescribing information for dose adjustments, if needed [see Drug Interactions (7.1)].

6 ADVERSE REACTIONS

The following clinically significant adverse reactions are described elsewhere in the labeling:

- Risk of Unintended Changes in Serum Calcium Levels Related to Number of Daily Injections [see Warnings and Precautions (5.1)]
- Serious Hypercalcemia [see Warnings and Precautions (5.2)]
- Serious Hypocalcemia [see Warnings and Precautions (5.3)]
- Potential Risk of Osteosarcoma [see Warnings and Precautions (5.4)]
- Orthostatic Hypotension [see Warnings and Precautions (5.5)]
- Risk of Digoxin Toxicity with Concomitant Use of Digitalis Compounds [see Warnings and Precautions (5.6)]

6.1 Clinical Trials Experience

Because clinical trials are conducted under widely varying conditions, adverse reaction rates observed in the clinical trials of a drug cannot be directly compared to rates in the clinical trials of another drug and may not reflect the rates observed in practice.

The phase 3 trial included 82 subjects with hypoparathyroidism with a median YORVIPATH treatment duration of 182 days (Study 1) [see Clinical Studies (14)].

Adverse reactions associated with YORVIPATH in Study 1 during the 26-week blinded period (incidence ≥5% and occurring ≥2% more frequently than placebo) are shown in Table 3.

Table 3: Adverse Reactions in ≥5% of Subjects with Hypoparathyroidism Treated with YORVIPATH and with ≥2% Higher Frequency Compared to Placebo in Study 1
Adverse Reaction | YORVIPATH N=61 n (%) | Placebo N=21 n (%)
Injection site reactions [Injection site reactions includes the preferred terms injection site bruising, injection site erythema, injection site rash, and injection site reaction.] | 24 (39) | 1 (5)
Vasodilatory signs and symptoms [Vasodilatory signs and symptoms includes the preferred terms blood pressure orthostatic decreased, dizziness, dizziness postural, orthostatic hypotension, palpitations, postural orthostatic tachycardia syndrome, presyncope, syncope, and vertigo.] | 17 (28) | 0
Headache | 13 (21) | 2 (10)
Diarrhea | 6 (10) | 1 (5)
Back pain [Back pain includes the preferred terms back pain, flank pain, and spinal pain.] | 5 (8) | 0
Hypercalcemia | 5 (8) | 0
Oropharyngeal pain | 4 (7) | 0
Abbreviations: N, total number of subjects in the treatment arm; n, number of subjects with the adverse reaction; %, percent of subjects with the adverse reaction.

Description of Selected Adverse Reactions

Hypercalcemia

Table 4 summarizes the number of subjects who had at least one serum calcium measurement greater than the upper limit of the reference range at a post-baseline visit in Study 1. The incidence of hypercalcemia was greater in subjects treated with YORVIPATH.

Symptomatic hypercalcemia was reported in 8% of subjects treated with YORVIPATH, and all occurred within the first 3 months after initiation of YORVIPATH.

Table 4: Incidence of Elevated Albumin-Corrected Serum Calcium (>10.6 mg/dL or >12 mg/dL) Post-Baseline in Subjects with Hypoparathyroidism Treated with YORVIPATH or Placebo in Study 1
 | YORVIPATH N=61 | Placebo N=21
Albumin-Corrected Serum Calcium >10.6 mg/dL, n (%) [Subjects meeting albumin-corrected serum calcium >10.6 mg/dL criterion includes subjects meeting albumin-corrected serum calcium >12 mg/dL criterion.] | 33 (54.1) | 2 (9.5)
Albumin-Corrected Serum Calcium >12 mg/dL, n (%) | 8 (13.1) | 0 (0)
Abbreviations: N, total number of subjects in the treatment arm; n, number of subjects meeting criteria.

7 DRUG INTERACTIONS

7.1 Drugs Affected by Serum Calcium

Digoxin

YORVIPATH increases serum calcium, therefore, concomitant use with digoxin (which has a narrow therapeutic index) may predispose patients to digitalis toxicity if hypercalcemia develops. Digoxin efficacy may be reduced if hypocalcemia is present. When YORVIPATH is used concomitantly with digoxin, measure serum calcium and digoxin levels, and monitor for signs and symptoms of digoxin toxicity. Adjustment of the digoxin and/or YORVIPATH dose may be needed.

7.2 Drugs Known to Affect Serum Calcium

Drugs that affect serum calcium may alter the therapeutic response to YORVIPATH. Measure serum calcium more frequently when YORVIPATH is used concomitantly with these drugs, particularly after these drugs are initiated, discontinued, or dose-adjusted.

8 USE IN SPECIFIC POPULATIONS

8.1 Pregnancy

Risk Summary

Available data from reports of pregnancies in the clinical trials from drug development are insufficient to identify a drug-associated risk of major birth defects, miscarriage, or other adverse maternal or fetal outcomes. There are disease-associated risks to the mother and fetus related to hypocalcemia in pregnancy (see Clinical Considerations). In animal reproduction studies, administration of palopegteriparatide to pregnant rats and rabbits during the period of organogenesis resulted in no significant adverse effects up to doses 16- and 13-fold, respectively, the maximum recommended human dose (MRHD), based on PTH(1-34) and active metabolite PTH(1-33) exposure by area under the curve (AUC) (see Data).

The background risk of birth defects and miscarriages for the indicated population is unknown. All pregnancies have a background risk of birth defect, loss, or other adverse outcomes. In the U.S. general population, the estimated background risk of major birth defects and miscarriages in clinically recognized pregnancies is 2% to 4% and 15% to 20%, respectively.

If YORVIPATH is administered during pregnancy, or if a patient becomes pregnant while receiving YORVIPATH, healthcare providers should report YORVIPATH exposure by calling 1-844-442-7236.

Clinical Considerations

Disease-Associated Maternal and Embryo/Fetal Risk

Maternal hypocalcemia can result in an increased rate of spontaneous abortion, premature and dysfunctional labor, and possibly preeclampsia. Infants born to mothers with hypocalcemia can have associated fetal and neonatal hyperparathyroidism, which may cause fetal and neonatal skeletal demineralization, subperiosteal bone resorption, osteitis fibrosa cystica, and neonatal seizures. Infants born to mothers with hypocalcemia should be monitored for signs of hypocalcemia or hypercalcemia, including neuromuscular irritability (e.g., myotonic jerks, seizures), apnea, cyanosis, and cardiac arrhythmias.

Data

Animal Data

In an embryo-fetal developmental toxicity study in rats, palopegteriparatide was administered subcutaneously during the period of organogenesis (gestation days (GD) 6 to 17) at doses of 2, 8, and 30 mcg/kg/day. In pregnant rats, there was no evidence of embryo-lethality, fetotoxicity, or fetal malformations up to the highest dose tested corresponding to 16-fold the MRHD, based on PTH(1-34) and active metabolite PTH(1-33) exposure by AUC.

In an embryo-fetal developmental toxicity study in rabbits, palopegteriparatide was administered subcutaneously to pregnant female rabbits during the period of organogenesis (GD 7 to 19) at doses of 1, 3, and 6 mcg/kg/day. There was no evidence of any palopegteriparatide-related embryo-lethality, fetotoxicity, or fetal malformations at any dose level up to 13-fold the MRHD, based on PTH(1-34) exposure by AUC.

8.2 Lactation

Risk Summary

There are no data available on the presence of palopegteriparatide or its metabolite in either human or animal milk, the effects on the breastfed infant, or the effects on milk production. Infants breastfed by females treated with YORVIPATH should be monitored for signs and symptoms of hypercalcemia or hypocalcemia. Monitoring of serum calcium in the infant should be considered.

The developmental and health benefits of breastfeeding should be considered along with the mother's clinical need for YORVIPATH and any potential adverse effects on the breastfed child from YORVIPATH or from the underlying sub-optimally treated maternal condition.

8.4 Pediatric Use

The safety and effectiveness of YORVIPATH have not been established in pediatric patients.

8.5 Geriatric Use

In Study 1, 8 of 61 (13%) YORVIPATH-treated subjects were 65 years of age or over compared to 2 of 21 (10%) subjects in the placebo group. Clinical studies of YORVIPATH did not include a sufficient number of subjects 65 years of age and older to determine whether they respond differently from younger adult subjects.

8.6 Renal Impairment

No dose adjustment is required in patients with mild, moderate, or severe renal impairment (estimated glomerular filtration rate ≥ 15 mL/min/1.73 m^2).

In a dedicated renal impairment study, patients with severe renal impairment (estimated glomerular filtration rate 15 to 30 mL/min/1.73 m^2) had no clinically significant difference in total PTH compared to subjects with normal renal function upon treatment with YORVIPATH [see Clinical Pharmacology (12.3)].

10 OVERDOSAGE

Accidental overdose of YORVIPATH may cause hypercalcemia that can be severe and require medical intervention. One subject in Study 1 accidentally received approximately 3-fold the prescribed dose of YORVIPATH for more than 7 consecutive days and developed albumin-corrected serum calcium as high as 16.1 mg/dL, requiring hospitalization.

11 DESCRIPTION

YORVIPATH (palopegteriparatide injection) is a parathyroid hormone analog (PTH(1-34)). Palopegteriparatide is a prodrug of teriparatide (PTH(1-34)) consisting of PTH(1-34) transiently conjugated to an inert carrier via a proprietary TransCon Linker. PTH(1-34) is identical to the 34 N-terminal amino acids (the biologically active region) of the 84-amino acid human parathyroid hormone. The carrier is a branched 40 kDa (2×20 kDa) methoxypolyethylene glycol (mPEG) moiety. The average molecular weight of palopegteriparatide is approximately 47.4 kDa.

The structure of palopegteriparatide drug substance is shown in Figure 2. The theoretical molecular formula is C209H340N60O59S3 + 2 × (C2H4O)n, where n is between approximately 450 and 500.

Figure 2: Structure of Palopegteriparatide

YORVIPATH is a sterile, clear, and colorless solution in a glass cartridge which is pre-assembled in a single-patient-use prefilled pen for subcutaneous administration. The prefilled pen is co-packaged with disposable needles to administer 14 doses of YORVIPATH. YORVIPATH is available in three presentations containing 0.56 mL, 0.98 mL, or 1.4 mL of YORVIPATH solution, and each pen presentation can deliver one of three distinct doses for 14 days of therapy.

Each mL of YORVIPATH solution contains 3456 mcg of palopegteriparatide, equivalent to 300 mcg of teriparatide (PTH(1-34)), and the following inactive ingredients: 41.7 mg mannitol, 2.5 mg metacresol, 0.13 mg sodium hydroxide, 1.18 mg succinic acid, and water for injection. YORVIPATH has a pH of 3.7 to 4.3.

Each pen of 0.56 mL contains 168 mcg teriparatide equivalent to 1935 mcg palopegteriparatide.

Each pen of 0.98 mL contains 294 mcg teriparatide equivalent to 3387 mcg palopegteriparatide.

Each pen of 1.4 mL contains 420 mcg teriparatide equivalent to 4838 mcg palopegteriparatide.

12 CLINICAL PHARMACOLOGY

12.1 Mechanism of Action

At physiological conditions, palopegteriparatide releases PTH(1-34) to maintain a continuous systemic exposure. Endogenous PTH maintains extracellular calcium and phosphate homeostasis by increasing serum calcium and decreasing serum phosphate. These effects are mediated by stimulating bone turnover to mobilize calcium and phosphate from bone, promoting renal calcium reabsorption and phosphate excretion, and facilitating active vitamin D synthesis, in turn increasing intestinal absorption of calcium and phosphate. Similar to endogenous PTH, PTH(1-34) released from palopegteriparatide exerts these effects through its main receptor, parathyroid hormone 1 receptor (PTH1R), which is highly expressed on osteoblasts, osteocytes, renal tubular cells, and in several other tissues.

12.2 Pharmacodynamics

Serum PTH(1-34) and serum calcium concentrations increased in a dose-related manner when YORVIPATH was administered to healthy volunteers. Exposure-response is not established in subjects with hypoparathyroidism.

Mean steady state concentration-time profile of albumin-corrected serum calcium concentrations over 24 hours following administration of YORVIPATH is presented in Figure 3.

Figure 3: Mean Steady-State Albumin-Corrected Serum Calcium Concentrations Following Subcutaneous Administration of YORVIPATH [Mean dose (range): 22.3 (12-33) mcg/day, n=7.] in Subjects with Hypoparathyroidism

The normal range for albumin-corrected serum calcium is 8.3 to 10.6 mg/dL.

12.3 Pharmacokinetics

YORVIPATH is a prodrug that releases PTH(1-34) via autocleavage of the TransCon linker.

PTH Cmax and AUC increased proportionally over a YORVIPATH dosage range of 12 to 24 mcg/day. PTH steady state is achieved after administration of YORVIPATH for 7 days.

Mean steady state concentration-time profile of PTH(1-34) over 24 hours following administration of YORVIPATH is presented in Figure 4. At steady state, administration of YORVIPATH resulted in continuous exposure to released PTH throughout the 24-hour dosing period.

Figure 4: Mean Steady State PTH(1-34) Following Subcutaneous Administration of YORVIPATH [Mean dose (range): 22.3 (12-33) mcg/day, n=7.] in Subjects with Hypoparathyroidism

a PTH(1-34) concentrations includes PTH(1-34) and active metabolite PTH(1-33).

Absorption

The median (range) time to reach maximum concentrations (Tmax) of PTH is 4 (4 to 8) hours.

Distribution

The estimated apparent volume of distribution (CV%) of palopegteriparatide is 4.8 (50) L. A similar distribution pattern as observed for endogenous PTH is expected for PTH released from palopegteriparatide.

Elimination

The apparent half-life of PTH released from palopegteriparatide is approximately 60 hours. The estimated clearance (CV%) of palopegteriparatide at steady state is 0.58 (52) L/day.

Metabolism

Released PTH includes PTH(1-34) and the active metabolite PTH(1-33). PTH(1-33) and PTH(1-34) have comparable affinity to and activation of PTH1R.

Specific Populations

There are no clinically significant differences in the pharmacokinetics of palopegteriparatide based on age, sex, or body weight. The data for race and ethnicity did not show any trends indicating differences, but the available data are too limited to make definitive conclusions.

Patients with Renal Impairment

A dedicated renal impairment study showed that mild, moderate, and severe renal impairment did not have a clinically significant impact on systemic exposure of total PTH following a single 50 mcg subcutaneous dose of palopegteriparatide. No studies were conducted in subjects with hypoparathyroidism who have severe renal impairment.

Patients with Hepatic Impairment

No dedicated hepatic impairment study was conducted. Mild and moderate hepatic impairment is not expected to have a clinically significant impact on the pharmacokinetics of palopegteriparatide.

12.6 Immunogenicity

The observed incidence of anti-drug antibodies is highly dependent on the sensitivity and specificity of the assay. Differences in assay methods preclude meaningful comparisons of the incidence of anti-drug antibodies in the studies described below with the incidence of anti-drug antibodies in other studies, including those of YORVIPATH or other teriparatide products.

Mean duration of exposure to YORVIPATH in clinical studies was 850 days. Of patients with post-baseline assessments, 0.7% (1 of 139 YORVIPATH-treated patients) had low titer, non-neutralizing antibodies towards PTH and 5% (7 of 139 YORVIPATH-treated patients) had low titer treatment-emergent antibodies against PEG. Three of 139 YORVIPATH-treated patients (2.2%) had pre-existing PEG antibodies that had a transient impact on the pharmacokinetics of palopegteriparatide and serum calcium, however, therapeutic effectiveness was maintained by dose adjustment of YORVIPATH using the trial titration algorithm.

13 NONCLINICAL TOXICOLOGY

13.1 Carcinogenesis, Mutagenesis, and Impairment of Fertility

Long-term animal studies to address the carcinogenic potential of palopegteriparatide have not been conducted.

Palopegteriparatide was not genotoxic in an in vitro bacterial reverse-mutation assay (Ames test), an in vitro human lymphocyte chromosome-aberration assay, and an in vivo rat bone-marrow micronucleus assay.

In fertility studies, palopegteriparatide was administered by subcutaneous injection at 2, 6, and 20 mcg/kg/day. Palopegteriparatide did not impair fertility in male and female rats up to the highest tested dose, which is 7-fold and 11-fold the MRHD, respectively, based on PTH(1-34) and active metabolite PTH(1-33) exposure by AUC.

13.2 Animal Pharmacology and Toxicology

In a 26-week rat study, daily subcutaneous administration of palopegteriparatide resulted in bone turnover imbalances in healthy euparathyroid rats. The bone effects tended towards a net catabolic effect (bone resorption) as evidenced by a decrease in proximal tibial trabecular bone volume and bone mineral content (BMC) in both sexes treated at the low dose of 5 mcg/kg/day (5-fold the MRHD, based on PTH(1-34) and active metabolite PTH(1-33) exposure by AUC) and in females treated at 10 mcg/kg/day (9-fold the MRHD, based on PTH(1-34) and PTH(1-33) exposure by AUC). A net anabolic bone effect (bone formation) including histologic increases in bone at several skeletal sites accompanied by increased osteoblast cellularity and increases in proximal tibia trabecular bone volume and BMC were observed in males at 10 mcg/kg/day (10-fold the MRHD, based on PTH(1-34) and PTH(1-33) exposure by AUC) and in both sexes treated at the high dose of 20 mcg/kg/day (19-fold the MRHD, based on PTH(1-34) and PTH(1-33) exposure by AUC). In a 4-week study in hypoparathyroid female rats, daily subcutaneous administration of palopegteriparatide at 5 and 10 mcg/kg/day (5- to 9-fold the MRHD, based on PTH(1-34) and PTH(1-33) exposure by AUC) resulted in a net catabolic bone effect as bone resorption (e.g., high urinary C-telopeptide of type 1 collagen, decreased tibial trabecular bone volume, increase in osteoclast surface, and endocortical eroded surface) appeared to exceed bone formation.

14 CLINICAL STUDIES

14.1 Treatment of Adults with Hypoparathyroidism

The effectiveness and safety of YORVIPATH in adults with hypoparathyroidism were evaluated in a 26-week, randomized, double-blind, placebo-controlled, phase 3 study (Study 1 [NCT04701203]).

Study 1 was conducted in 82 subjects with hypoparathyroidism. Prior to randomization, all subjects underwent an approximate 4-week screening period in which calcium and active vitamin D supplements were adjusted to achieve an albumin-corrected serum calcium concentration between 7.8 and 10.6 mg/dL, a magnesium concentration ≥1.3 mg/dL and below the upper limit of the reference range, and a 25(OH) vitamin D concentration between 20 to 80 ng/mL. During the double-blind period, subjects were randomized to either YORVIPATH (N = 61) or placebo (N= 21), at a starting dose of 18 mcg/day, co-administered with conventional therapy (calcium and active vitamin D). Randomization was stratified by etiology of hypoparathyroidism (postsurgical vs. all other causes). Study drug and conventional therapy were subsequently titrated according to the albumin-corrected serum calcium levels [see Dosage and Administration (2.3, 2.4)].

The mean age at enrollment was 49 years (range: 19 to 78 years), 78% were female, and 93% were Caucasian. Eighty-five percent (85%) of subjects had hypoparathyroidism acquired from neck surgery. Of the subjects with other etiologies of hypoparathyroidism, 7 (8.5%) subjects had idiopathic disease, 2 had autoimmune polyglandular syndrome type 1 (APS-1), 1 had autosomal dominant hypocalcemia type 1 (ADH1, CaSR mutation), 1 had DiGeorge Syndrome, and 1 had hypoparathyroidism, sensorineural deafness and renal dysplasia (HDR) syndrome (GATA3 mutation). At baseline, the median duration of hypoparathyroidism was 8.5 years (range 1 to 56 years). Baseline mean albumin-corrected serum calcium was 8.8 mg/dL and 8.6 mg/dL and mean 24-hour urine calcium was 392 mg/day and 329 mg/day for YORVIPATH and placebo, respectively. The mean baseline dose of elemental calcium was 1839 mg/day, and the mean baseline doses of active vitamin D were 0.75 mcg/day in calcitriol-treated subjects (n=70), and 2.3 mcg/day in alfacalcidol-treated subjects (n=12).

Efficacy Assessment and Results

Efficacy was assessed based on the proportion of subjects who achieved all of the following at Week 26:

- Albumin-corrected serum calcium in the normal range (8.3 to 10.6 mg/dL),
- Independence from conventional therapy (defined as requiring no active vitamin D and ≤600 mg/day of calcium supplementation, including no use of pro re nata [PRN] doses) since Week 22,
- No increase in the study drug dose since Week 22,
- No missing active vitamin D and calcium data since Week 22, and
- Study drug dose of 30 mcg or less once daily during the 26-week treatment period

In the YORVIPATH group, 68.9% (42/61) of subjects met the efficacy endpoint at Week 26 compared with 4.8% (1/21) of subjects in the placebo group. The treatment difference was 64.2% (95% confidence interval: 49.5%, 78.8%) (Table 5).

Table 5: Efficacy at Week 26 in Adults with Hypoparathyroidism in Study 1
 | YORVIPATH (N=61) | Placebo (N=21) | Response Rate Difference (95% CI)
Overall Response at Week 26 | 42 (68.9%) | 1 (4.8%) | 64.2% (49.5%, 78.8%)
Response for each component
Normal albumin-corrected serum calcium [Normal range for albumin-corrected serum calcium was 8.3 to 10.6 mg/dL.] | 49 (80.3%) | 10 (47.6%) | 32.7% (9.2%, 56.3%)
Independence from active vitamin D [No daily standing doses of active vitamin D, no PRN doses, and no missing active vitamin D data within 4 weeks prior to Week 26 visit.] | 58 (95.1%) | 5 (23.8%) | 71.3% (52.5%, 90.2%)
Independence from therapeutic dose of calcium [Average daily standing dose of elemental calcium ≤600 mg, no PRN doses, and no missing calcium data within 4 weeks prior to Week 26 visit.] | 53 (86.9%) | 1 (4.8%) | 82.2% (70.0%, 94.4%)
No increase in study drug dose since Week 22 [No increase in study drug dose within 4 weeks prior to Week 26 visit.] | 57 (93.4%) | 12 (57.1%) | 36.4% (14.2%, 58.5%)
Study drug dose ≤30 mcg/day up to Week 26 [Subjects who received more than 30 mcg/day at any timepoint during the 26-week treatment period were considered as non-responders for the efficacy endpoint.] | 56 (91.8%) | NA | NA
Abbreviations: CI: confidence interval; NA: not applicable; PRN: pro re nata.

The proportion of subjects randomized to YORVIPATH who met the efficacy endpoint decreased over time as follows: 68.9% (42/61) at Week 26 and 39.3% (24/61) at both Week 52 and Week 78 during the open-label extension period. Allowing for dose up-titration, the proportion of subjects who were able to maintain normocalcemia and independence from active vitamin D and therapeutic dose of calcium was 64% (39/61) at Week 52 and 66% (40/61) at Week 78.

16 HOW SUPPLIED/STORAGE AND HANDLING

16.1 How Supplied

YORVIPATH is available in a prefilled, disposable, 14-dose pen-injector (Table 6). Each pen contains a clear and colorless solution of 3456 mcg/mL of palopegteriparatide equivalent to 300 mcg/mL of teriparatide. Each pack contains 2 prefilled pens and 28 needles for 28 injections (plus two spare needles).

Table 6: YORVIPATH Prefilled Pen Presentations
Prefilled Pen Presentation | Labeled Doses | Content of Pack | NDC
YORVIPATH (168 mcg/0.56 mL) identified by blue push button | 6, 9, and 12 mcg | 2 prefilled pens 30 needles | 73362-100-01
YORVIPATH (294 mcg/0.98 mL) identified by orange push button | 15, 18, and 21 mcg | 2 prefilled pens 30 needles | 73362-101-01
YORVIPATH (420 mcg/1.4 mL) identified by burgundy push button | 24, 27, and 30 mcg | 2 prefilled pens 30 needles | 73362-102-01

16.2 Storage and Handling

Do not freeze. Store away from heat. Keep YORVIPATH in the packaging to protect from light.

Until first use, store YORVIPATH in the refrigerator between 2°C to 8°C (36°F to 46°F).

After first use, store YORVIPATH for 14 days at room temperature below 30°C (86°F). After each use, remove the needle and put the pen cap on to protect from light. Discard the prefilled pen 14 days after first use.

17 PATIENT COUNSELING INFORMATION

Advise the patient to read the FDA-approved patient labeling (Medication Guide and Instructions for Use).

Dosage and Administration

Advise patients to use only one injection to achieve the once daily recommended dosage [see Dosage and Administration (2.1) and Warnings and Precautions (5.1)].

Advise patients that the healthcare provider may change the dose of YORVIPATH, calcium, or active vitamin D supplements based on serum calcium levels.

Advise patients to administer YORVIPATH subcutaneously to the abdomen or front of the thigh. Advise patients to rotate the injection site daily [see Dosage and Administration (2.6)].

Adverse Reactions

Risk of YORVIPATH Adverse Reactions with Use of Two Injections to Achieve the Recommended Once Daily Dosage

Advise patients that using two YORVIPATH injections to achieve the recommended once daily dosage increases the variability of the total delivered dose, which can cause unintended changes in serum calcium levels, including hypercalcemia and hypocalcemia. Advise patients to use only one YORVIPATH injection to achieve the recommended once daily dosage [see Warnings and Precautions (5.1)].

Serious Hypercalcemia and Serious Hypocalcemia

Advise patients taking YORVIPATH to contact their healthcare provider promptly if they develop symptoms of hypercalcemia (e.g., nausea, vomiting, constipation, lethargy, muscle weakness) or hypocalcemia, to report abrupt discontinuations in YORVIPATH dosing, and to follow recommended serum calcium monitoring [see Warnings and Precautions (5.2, 5.3)].

Potential Risk of Osteosarcoma

Advise patients that administration of other PTH products causes an increase in the incidence of osteosarcoma in rats. No increased risk of osteosarcoma was observed with teriparatide compared to a general population. Advise patients to promptly report clinical symptoms (e.g., persistent localized pain) and signs (e.g., soft tissue mass tender to palpation) that could be consistent with osteosarcoma [see Warnings and Precautions (5.4)].

Orthostatic Hypotension

When initiating YORVIPATH treatment, advise patients to be prepared to immediately sit or lie down during or after administration if they feel lightheaded or have palpitations after the injection until their symptoms resolve. If these symptoms persist or worsen, advise patients to consult their healthcare provider [see Warnings and Precautions (5.5)].

Digoxin Toxicity

Advise patients to report use of a digoxin-containing medication and to follow recommended serum calcium and digoxin monitoring [see Warnings and Precautions (5.6)].

Hypersensitivity

Advise patients that serious hypersensitivity reactions (including anaphylaxis and angioedema) are possible with PTH products. Advise patients to discontinue YORVIPATH and promptly seek medical attention if signs or symptoms of hypersensitivity reaction occur [see Contraindications (4)].

Pregnancy

Advise females who are exposed to YORVIPATH during pregnancy that there is a pregnancy safety study that monitors pregnancy outcomes. Encourage these patients to report their pregnancy to Ascendis Pharma (1-844-442-7236) [see Use in Specific Populations (8.1)].

©2024 Ascendis Pharma. All rights reserved. YORVIPATH®, Ascendis®, TransCon®, and Ascendis Pharma logo and the company logo are trademarks owned by the Ascendis Pharma Group.

PATENT INFORMATION: www.ascendispharma.us/products/patents

Manufactured by:
Ascendis Pharma Bone Diseases A/S
Tuborg Boulevard 12, DK-2900 Hellerup, Denmark

For information about YORVIPATH contact:
Ascendis Pharma Endocrinology, Inc.
212 Carnegie Center, Suite 301
Princeton, New Jersey 08540, USA
1-844-442-7236 (1-844-44ASCENDIS)
www.YORVIPATH.com

MEDICATION GUIDE
YORVIPATH® (YOR-vih-path)
(palopegteriparatide)
injection, for subcutaneous use

What is the most important information I should know about YORVIPATH?
YORVIPATH may cause serious side effects, including:

- High levels of calcium in the blood (hypercalcemia). YORVIPATH can cause some people to have higher blood calcium levels than normal. Your health care provider should check your blood calcium before you start and during your treatment with YORVIPATH. Tell your health care provider if you have nausea, vomiting, dizziness, feeling thirsty, confusion, muscle weakness, and irregular heartbeat. Hypercalcemia is more likely to occur within the first 3 months of starting YORVIPATH, but it may occur at any time.
- Low levels of calcium in the blood (hypocalcemia). People who stop using, miss, or change a dose of YORVIPATH may have an increased risk of low blood calcium levels, but hypocalcemia may occur at any time. Tell your health care provider if you have tingling in your fingertips, toes, lips or tongue, muscle spasms or cramps, oral numbness, depression, have problems thinking or remembering, abnormal heart rhythms, and seizures.
- Possible bone cancer (osteosarcoma). Tell your health care provider right away if you have pain in any areas of your body that does not go away or any new or unusual lumps or swelling under your skin that is tender to touch. These are some of the signs and symptoms of osteosarcoma and your health care provider may need to do further tests.

Tell your health care provider right away if you have any of these signs and symptoms of osteosarcoma, or high or low blood calcium levels.
See "What are the possible side effects of YORVIPATH?" for information about side effects.

What is YORVIPATH?

- YORVIPATH is a prescription medicine used to treat adults with low parathyroid hormone (PTH) (hypoparathyroidism).

It is not known if YORVIPATH is safe and effective in people who have been recently diagnosed with hypoparathyroidism after surgery.
It is not known if YORVIPATH is safe and effective if it is started in people with low levels of calcium in the blood.
It is not known if YORVIPATH is safe and effective in children.
YORVIPATH should not be used in children and young adults whose bones are still growing.

Who should not take YORVIPATH?
Do not use YORVIPATH if you:

- are allergic to palopegteriparatide or any of the other ingredients in YORVIPATH. See the end of this Medication Guide for a complete list of ingredients in YORVIPATH.

Before using YORVIPATH, tell your health care provider about all of your medical conditions, including if you:

- are at higher risk of a type of bone cancer called osteosarcoma. This is especially important:
  - if you have a bone disease that increases your risk of developing osteosarcoma (including if you have Paget's disease).
  - if a blood test shows that you have unexplained increases in bone alkaline phosphatase.
  - if you have cancer of the bones or other cancer that has spread to your bones.
  - if you are having or have had radiation therapy to the skeleton.
  - if you are affected with a condition that runs in your family that can increase your chance of getting cancer in your bones.
- take medicines that contain digoxin.
- take medicines used to treat osteoporosis.
- take medicines that can affect calcium levels in your blood.
- are pregnant or plan to become pregnant. It is not known if YORVIPATH will harm your unborn baby.
  - Tell your health care provider if you become pregnant during treatment with YORVIPATH.
  - If you become pregnant while being treated with YORVIPATH, you are encouraged to enroll in the Pregnancy Safety Study. The purpose of the pregnancy safety study is to collect information about the health of you and your baby. Contact Ascendis Pharma at 1-844-442-7236 as soon as you learn that you are pregnant or ask your health care provider to contact them for you.
- are breastfeeding or plan to breastfeed. It is not known if YORVIPATH passes into your breast milk. Talk to your health care provider about the best way to feed your baby during treatment with YORVIPATH.

Tell your health care provider about all the medicines you take, including prescription and over-the-counter medicines, vitamins, and herbal supplements. YORVIPATH and other medicines may affect each other causing side effects. Know the medicines you take. Keep a list of them to show your health care provider and pharmacist when you get a new medicine.

How should I use YORVIPATH?

- Read the detailed Instructions for Use that comes with YORVIPATH.
- Use YORVIPATH exactly as your health care provider tells you to take it.
- Before you use YORVIPATH for the first time, a health care provider should show you how to use the pen the right way.
- Some people may feel dizzy, get a fast heartbeat, or feel light-headed right after injecting YORVIPATH. For the first few doses, give your injection of YORVIPATH in a place where you can sit or lie down right away if you get these symptoms. If your symptoms get worse or do not go away, contact your health care provider before you continue using YORVIPATH.
- Do not stop taking or change your dose of YORVIPATH unless your health care provider tells you to. The levels of calcium in your blood may change, and you may develop symptoms. See "What are the possible side effects of YORVIPATH?"
- Give no more than 1 YORVIPATH injection each day in your belly (abdomen) or in the front of the thigh just under your skin (subcutaneous). Inject into a different area each day to help avoid damaging your skin.
- Throw away each pen 14 days after first use.
- YORVIPATH is colorless. Do not use YORVIPATH if you notice that the solution is cloudy, colored, or has visible particles in it.
- Your health care provider should check your blood calcium level when you start and while you are using YORVIPATH. After you start YORVIPATH, your health care provider may change your doses of calcium and active vitamin D.
- If you miss a day or forget to inject your daily dose of YORVIPATH, you can inject the dose as soon as you remember if less than 12 hours have passed. If the dose has been missed by more than 12 hours, skip the missed dose and continue injecting your next dose as you normally would.

What are the possible side effects of YORVIPATH?
YORVIPATH may cause serious side effects:

- See "What is the most important information I should know about YORVIPATH?"
- Allergic (hypersensitivity) reaction, including anaphylaxis. Stop taking YORVIPATH and tell your health care provider or get emergency medical help right away if you have any of the following symptoms of an allergic reaction:

- swelling of your face, lips, mouth, or tongue
- breathing problems
- fainting, dizziness, feeling lightheaded (low blood pressure)

- fast heartbeat
- itching
- rash
- hives

- Decrease in blood pressure when you change positions (orthostatic hypotension). Some people may feel dizzy, get a fast heartbeat, or feel light-headed right after injecting YORVIPATH. For the first few doses, give your injection of YORVIPATH in a place where you can sit or lie down right away if you get these symptoms. If your symptoms get worse or do not go away, contact your health care provider before you continue using YORVIPATH.
- Digoxin toxicity if you are using digoxin and YORVIPATH at the same time. Tell your health care provider if you experience irregular heart rhythm, heart palpitations, confusion, loss of appetite, nausea, vomiting, diarrhea, or vision problems.

The most common side effects of YORVIPATH include injection site reactions, vasodilatory signs or symptoms such as a drop in blood pressure or lightheadedness when standing up, headache, diarrhea, back pain, high calcium levels, and sore throat.
These are not all of the possible side effects of YORVIPATH. Call your doctor for medical advice about side effects. You may report side effects to FDA at 1-800-FDA-1088.

How should I store YORVIPATH?

- Before first use, store YORVIPATH in a refrigerator between 36°F to 46°F (2°C to 8°C). Do not freeze. Store away from heat. Store in the package with the pen cap on in order to protect from light.
- After first use, store at room temperature below 86°F (30°C). Keep the pen cap on the prefilled pen in order to protect from light. Throw away each pen 14 days after first use.

Keep YORVIPATH and all medicines out of the reach of children.

General information about the safe and effective use of YORVIPATH.
Medicines are sometimes prescribed for purposes other than those listed in a Medication Guide. Do not use YORVIPATH for a condition for which it was not prescribed. Do not give YORVIPATH to other people, even if they have the same symptoms that you have. It may harm them. You can ask your pharmacist or health care provider for information about YORVIPATH that is written for health professionals.

What are the ingredients in YORVIPATH?
Active ingredient: palopegteriparatide
Inactive ingredients: mannitol, metacresol, sodium hydroxide, succinic acid, and water for injection.
Manufactured by: Ascendis Pharma Bone Diseases A/S, Denmark
YORVIPATH® is a registered trademark of Ascendis Pharma Group.
For more information, go to www.YORVIPATH.com or call 1-844-442-7236.

This Medication Guide has been approved by the U.S. Food and Drug Administration

Approved: 08/2024

INSTRUCTIONS FOR USE

Label

Content

FRONT

INSTRUCTIONS FOR USE
Yorvipath®
(palopegteriparatide)
injection, for subcutaneous use
For 6, 9 or 12 mcg doses only
This Instructions for Use contains information on how to inject YORVIPATH
168 mcg/0.56 mL (300 mcg/mL) prefilled pen for 6, 9 or 12 mcg doses only
ascendis pharma

Back

Additional information
If you need help, please ask your health care provider or nurse for advice or contact the Ascendis Pharma Helpline:
Ascendis Pharma Helpline:
Toll-free telephone number:
1-844-442-7236
Ascendis Pharma Bone Diseases A/S
Tuborg Boulevard 12
DK-2900 Hellerup
Denmark
ascendis pharma

Panel 1

1. How often must I test the pen flow?
You should only test the pen flow (Section 2) the first time you use a new pen (or if you think it might be damaged) to not waste medicine. The test checks to make sure the medicine flows through the pen so that you get the right doses of medicine.
2. I do not see drops appear after I have tested the pen flow 5 times. What should I do?
If you see no drop on the needle tip after 5 attempts it might be because there is no flow through the pen and needle.
Change the needle (see Section 5, Step 12) and test the pen flow again (see Section 2, Steps A-C). You can be sure the flow works correctly when you see the drop of medicine.
If it still does not work, throw away (discard) the pen and contact your health care provider.
3. How do I know I have completed the injection?
Your injection is only completed after you have pressed the push button all the way in and the dose selector has rotated back to the "•" and you have kept the needle in the skin for 5 seconds.
4. Why do I have to keep holding the pen in the skin for 5 seconds?
Some medicine might flow back into the pen or flow backward from the injection site and be left on the skin.
Holding the pen in the skin for 5 seconds helps to make sure that all the medicine has been injected.
5. I cannot dial the dose selector to the required dose. What should I do?
The pen does not allow a larger dose to be set than what is left in the pen.
If your dose is larger than the amount of medicine left in the pen you will not be able to dial a full dose. You must throw away your pen and take the full dose of medicine with a new pen.

Panel 2

- Until first use, refrigerate your pens between 2°C to 8°C (36°F to 46°F) and keep in the package to protect from light.
- After first use, store your pen for 14 days at room temperature below 30°C (86°F).
- Do not leave your pen in a car or another place where it can get too hot or too cold.
- Do not freeze your pen.
- Store YORVIPATH away from heat.
- Keep the YORVIPATH pen out of the reach of children.

Tip: You should take a new pen out of the refrigerator 20 minutes before first use to allow the medicine to get to room temperature before injecting.

Panel 3

Caring For Your Pen

- Handle your pen with care.
- Keep your pen dry.
- Use a moist cloth to clean your pen.
- Do not drop or knock your pen against hard surfaces. If you do, test the pen flow again (Section 2, Steps A – C) before next use.
- Do not apply extra force to your pen. It might be empty, damaged and no longer works properly.
- Do not attempt to repair a damaged pen yourself. If your pen is damaged, contact the Ascendis Pharma Helpline.

Panel 4

Important Information You Need To Know
Before Using Your YORVIPATH Pen
Read and follow this Instructions for Use carefully so that you inject YORVIPATH the right way.
If you do not understand or are unable to complete a step that is described in this Instructions for Use, contact your health care provider or nurse or the Ascendis Pharma Helpline.
Make sure you have received training from your health care provider or nurse before injecting. This is important to make sure that you get the correct treatment.
Inject YORVIPATH into the belly (abdomen) or in the front of the thigh.
Your pen can deliver doses of 6, 9 or 12 mcg. It is used for injections under the skin (subcutaneous) for daily treatment of hypoparathyroidism. Your pen is a prefilled dial-a-dose throw away (disposable) pen.
It contains medicine for 14 days of use and is intended to be used 1 time each day. Do not use more than one injection to achieve the recommended once daily dosage.
You can dial doses of 6, 9 or 12 mcg with the pen.
For Correct Use
If you are blind or visually impaired or if you have lack of concentration do not use your pen without help. Get help from a person who is trained to use the YORVIPATH pen. Store your pen out of the reach of children and any other persons who do not know how to handle it properly.

Panel 5

- Only use your pen as directed by your health care provider or nurse.
- The pen and needles are for single-patient use only. Do not share your pen or needles with other people. It might lead to infection (cross-contamination).
- Start by checking your pen to make sure it is the correct pen.
- Always check the expiration date on the pen label and needle foil before use.
- Always inspect the pen visually before use to make sure it is not damaged and medicine is clear, colorless and without particles.
- Always use a new needle for each injection.
- Only inject into the abdomen or front of thigh as instructed by your health care provider or nurse. Remember to change injection site for each injection and avoid skin that is red, swollen or scarred.
- Always keep the cap on the pen when it is not in use to protect the medicine from light.
- Remove the needle after every use. Do not store the pen with the needle on.
- Always throw away your pen after 14 days of use, even if it still has medicine left inside. This is important to make sure that you get the right effect of your medicine.
- By failing to follow these instructions you may not get the right dose and may therefore not get the full effect of your medicine.
- Avoid bending or breaking off the pen needle.
- Do not change the injection angle after the needle has been inserted into the skin. Changing the angle can cause the needle to bend or break off. A bent or broken needle can remain stuck in the body or remain completely under the skin. If a broken needle remains stuck in the body or remains under the skin, seek medical help right away.

Panel 6

Compatible Pen Needles
In each of the two inner boxes there are 15 disposable Unifine© Pentips© Needles (31G × 5mm) together with a YORVIPATH prefilled pen for doses of 6, 9 or 12 mcg.
Always use the needles that come with YORVIPATH pen for your injections.
For Correct Disposal
Always put your used YORVIPATH needles in an FDA-cleared sharps disposal container right away after use. Always put your used pen in an FDA-cleared sharps disposal container after 14 days of use.
Do not throw away (dispose of) YORVIPATH in your household trash.
If you do not have an FDA-cleared sharps disposal container, you may use a household container that is:

- made of heavy-duty plastic.
- can be closed with a tight-fitting, puncture resistant lid, without sharps being able to come out.
- upright and stable during use.
- leak-resistant.
- properly labeled to warn of hazardous waste inside the container.

When your sharps disposal container is almost full, you will need to follow your community guidelines for the right way to dispose of your sharps disposal container. For more information about the safe sharps disposal, and for specific information about sharps disposal in the state that you live in, go to the FDA's website at: http://www.fda.gov/safesharpsdisposal. Do not dispose of your used sharps disposal container in your household trash unless your community guidelines permit this. Do not recycle your used sharps disposal container.

Panel 7

Parts Overview
Figure A
Symbols:
-Droplets
-Doses (6, 9 or 12 mcg)
-End-of-dose
-Pen cap
-Inspection window (medicine inside)
-Pen
-Pen label
-Push button
-Dose selector
-Dose window
-Single Use Needle
-Outer needle cover
-Inner Needle shield
-Needle tip
-Needle
-Foil
You Will Also Need
Figure B
Sharps disposal container
Alcohol wipe

Panel 8

1 Prepare Pen And Needle
Step 1
Wash your hands with soap and water before using YORVIPATH pen. Take your YORVIPATH pen and a needle from the box and check the expiration date on both pen and needle (see Figure C). Do not use if expired.

Figure C

Expiration date OK?
Step 2
Pull off the pen cap and check the inspection window to make sure the medicine inside the pen is clear and colorless (see Figure D).
Important: If the medicine has visible particles in it do not use the pen. Use a new pen.

Figure D

Medicine OK?
Step 3
Pull the foil off the needle (see Figure E). This needle can only be used 1 time.

Figure E

Step 4
Attach the needle straight on to your pen, then screw the needle onto the pen until secure (see Figure F).

Figure F

Step 5

1. Pull off the outer needle cover and
  keep this for later needle removal (see Figure G: a).
2. Pull off the inner needle shield
  and throw this away (see Figure G: b).

Figure G

Panel 9

2 If New Pen, Test Pen Flow

Day 1
Attention
Only test pen flow (Steps A – C) the first time you use a new pen.
If your pen is already in use, go to section "3 Prepare Injection".

Step A

Turn the dose selector clockwise (to the right) 2 clicks until you see the droplet symbol "" in the dose window (see Figure H).

Note: You can always correct the selection by turning the dose selector.

Figure H

Step B
Make any air bubbles rise to the top of the pen by tapping the inspection window (see Figure I). Keep the pen with the needle tip pointed up.
Note: Tiny air bubbles are ok.

Figure I

tap tap
Step C
Press the push button and watch drops of medicine come out of the needle tip. When you press, make sure that the dose selector rotates back to the symbol "•" (see Figure J).
Important: If you do not see drops of medicine, repeat this test (Steps A – C) up to 5 times. If drops are still not seen, change the needle and repeat the test.

Figure J

Panel 10

3 Prepare Injection and Select Dose
Step 6
Choose injection site. There are two regions of your body you can inject into (see Figure K).
Avoid injecting where skin is red, swollen or scarred. Choose a different injection site each time you inject.

Figure K

Front
Stomach (Abdomen) at least 2 inches away from the belly button
Thighs
Step 7
Wash your hands and clean the injection site with an alcohol wipe (see Figure L).

Figure L

Use alcohol wipe
Step 8
Select your dose as prescribed by your health care provider (6, 9 or 12 mcg) by turning the dose selector clockwise (to the right) (see Figure M).
Important: Make sure not to press the push button while selecting your dose to not spill medicine.
Note: Always throw away your pen and use another pen if you cannot dial a full dose.

Figure M

Panel 11

4 Inject Dose
Attention
Use the injection technique recommended by your health care provider or nurse.
Read this whole section (Steps 9 - 11) before you start to inject.
Step 9
Make sure you can see the dose window.
Insert the needle into the skin
(see Figure N).

Figure N

Step 10
Press the push button all the way in and hold steady for 5 seconds. Make sure the dose selector rotates back to the symbol "●". This means that you have given the full dose (see Figure O).

Figure O
Pres…
then hold 5 seconds.

Step 11
Slowly remove the pen from the injection site (see Figure P).

Figure P

Panel 12

5 Throw Away Used Needle
Step 12
Reattach the outer needle cover to carefully remove the needle. Insert the needle tip into the outer needle cover and secure the outer needle cover onto the needle (see Figure Q).
Important: Always reattach the outer needle cover before removing the needle to reduce the risk of needle stick and cross-contamination.

Figure Q

Step 13

Unscrew the needle and throw away the needle safely in accordance with local regulations (see Figure R).

Figure R

Step 14
Click the pen cap firmly onto the pen to protect it between injections and to protect the medicine from light (see Figure S).

Figure S

click!

Panel 13

6 Throw Away Used Pen
Day 14
Important: Always throw away the pen 14 days after first use according to local regulations.
Always throw away your pen and any extra needles after 14 days of use, even if it still has medicine inside (see Figure T). This is important to make sure that you get the full effect of your medicine.

Figure T

This instructions for Use has been approved by the U.S. Food and Drug Administration.
Approved 10/2025

INSTRUCTIONS FOR USE

Label

Content

FRONT

INSTRUCTIONS FOR USE
Yorvipath®
(palopegteriparatide)
injection, for subcutaneous use
For 15, 18 or 21 mcg doses only
This Instructions for Use contains information on how to inject YORVIPATH
294 mcg/0.98 mL (300 mcg/mL) prefilled pen for 15, 18 or 21 mcg doses only
ascendis pharma

Back

Additional information
If you need help, please ask your health care provider or nurse for advice or contact the Ascendis Pharma Helpline:
Ascendis Pharma Helpline:
Toll-free telephone number:
1-844-442-7236
Ascendis Pharma Bone Diseases A/S
Tuborg Boulevard 12
DK-2900 Hellerup
Denmark
ascendis pharma

Panel 1

Troubleshooting
1. How often must I test the pen flow?
You should only test the pen flow (Section 2) the first time you use a new pen (or if you think it might be damaged) to not waste medicine. The test checks to make sure the medicine flows through the pen so that you get the right doses of medicine.
2. I do not see drops appear after I have tested the pen flow 5 times. What should I do?
If you see no drop on the needle tip after 5 attempts it might be because there is no flow through the pen and needle.
Change the needle (see Section 5, Step 12) and test the pen flow again (see Section 2, Steps A-C). You can be sure the flow works correctly when you see the drop of medicine.
If it still does not work, throw away (discard) the pen and contact your health care provider.
3. How do I know I have completed the injection?
Your injection is only completed after you have pressed the push button all the way in and the dose selector has rotated back to the "•" and you have kept the needle in the skin for 5 seconds.
4. Why do I have to keep holding the pen in the skin for 5 seconds?
Some medicine might flow back into the pen or flow backward from the injection site and be left on the skin. Holding the pen in the skin for 5 seconds helps to make sure that all the medicine has been injected.
5. I cannot dial the dose selector to the required dose. What should I do?
The pen does not allow a larger dose to be set than what is left in the pen. If your dose is larger than the amount of medicine left in the pen you will not be able to dial a full dose. You must throw away your pen and take the full dose of medicine with a new pen.

Panel 2

- Until first use, refrigerate your pens between 2°C to 8°C (36°F to 46°F) and keep in the package to protect from light.
- After first use, store your pen for 14 days at room temperature below 30°C (86°F).
- Do not leave your pen in a car or another place where it can get too hot or too cold.
- Do not freeze your pen.
- Store YORVIPATH away from heat.
- Keep the YORVIPATH pen out of the reach of children.

Tip: You should take a new pen out of the refrigerator 20 minutes before first use to allow the medicine to get to room temperature before injecting.

Panel 3

Caring For Your Pen

- Handle your pen with care.
- Keep your pen dry.
- Use a moist cloth to clean your pen.
- Do not drop or knock your pen against hard surfaces. If you do, test the pen flow again (Section 2, Steps A – C) before next use.
- Do not apply extra force to your pen. It might be empty, damaged and no longer works properly.
- Do not attempt to repair a damaged pen yourself. If your pen is damaged, contact the Ascendis Pharma Helpline.

Panel 4

Important Information You Need To Know Before Using Your YORVIPATH Pen
Read and follow this Instructions for Use carefully so that you inject YORVIPATH the right way.
If you do not understand or are unable to complete a step that is described in this Instructions for Use, contact your health care provider or nurse or the Ascendis Pharma Helpline.
Make sure you have received training from your health care provider or nurse before injecting. This is important to make sure that you get the correct treatment.
Inject YORVIPATH into the belly (abdomen) or in the front of the thigh.
Your pen can deliver doses of 15, 18 or 21 mcg. It is used for injections under the skin (subcutaneous) for daily treatment of hypoparathyroidism. Your pen is a prefilled dial-a-dose throw away (disposable) pen.
It contains medicine for 14 days of use and is intended to be used 1 time each day. Do not use more than one injection to achieve the recommended once daily dosage.
You can dial doses of 15, 18 or 21 mcg with the pen.
For Correct Use
If you are blind or visually impaired or if you have lack of concentration do not use your pen without help. Get help from a person who is trained to use the YORVIPATH pen.
Store your pen out of the reach of children and any other persons who do not know how to handle it properly.

Panel 5

- Only use your pen as directed by your health care provider or nurse.
- The pen and needles are for single-patient use only. Do not share your pen or needles with other people. It might lead to infection (cross-contamination).
- Start by checking your pen to make sure it is the correct pen.
- Always check the expiration date on the pen label and needle foil before use.
- Always inspect the pen visually before use to make sure it is not damaged and medicine is clear, colorless and without particles.
- Always use a new needle for each injection.
- Only inject into the abdomen or front of thigh as instructed by your health care provider or nurse. Remember to change injection site for each injection and avoid skin that is red, swollen or scarred.
- Always keep the cap on the pen when it is not in use to protect the medicine from light.
- Remove the needle after every use. Do not store the pen with the needle on.
- Always throw away your pen after 14 days of use, even if it still has medicine left inside. This is important to make sure that you get the right effect of your medicine.
- By failing to follow these instructions you may not get the right dose and may therefore not get the full effect of your medicine.
- Avoid bending or breaking off the pen needle.
- Do not change the injection angle after the needle has been inserted into the skin. Changing the angle can cause the needle to bend or break off. A bent or broken needle can remain stuck in the body or remain completely under the skin. If a broken needle remains stuck in the body or remains under the skin, seek medical help right away.

Panel 6

Compatible Pen Needles
In each of the two inner boxes there are 15 disposable Unifine© Pentips© Needles (31G × 5mm) together with a YORVIPATH prefilled pen for doses of 15, 18 or 21 mcg. Always use the needles that come with YORVIPATH pen for your injections.
For Correct Disposal
Always put your used YORVIPATH needles in an FDA-cleared sharps disposal container right away after use. Always put your used pen in an FDA-cleared sharps disposal container after 14 days of use.
Do not throw away (dispose of) YORVIPATH in your household trash.
If you do not have an FDA-cleared sharps disposal container, you may use a household container that is:

- made of heavy-duty plastic.
- can be closed with a tight-fitting, puncture resistant lid, without sharps being able to come out.
- upright and stable during use.
- leak-resistant.
- properly labeled to warn of hazardous waste inside the container.

When your sharps disposal container is almost full, you will need to follow your community guidelines for the right way to dispose of your sharps disposal container. For more information about the safe sharps disposal, and for specific information about sharps disposal in the state that you live in, go to the FDA's website at: http://www.fda.gov/safesharpsdisposal. Do not dispose of your used sharps disposal container in your household trash unless your community guidelines permit this. Do not recycle your used sharps disposal container.

Panel 7

Parts Overview
Figure A
Symbols:
-Droplets
-Doses (15, 18 or 21 mcg)
-End-of-dose
-Pen cap
-Inspection window (medicine inside)
-Pen
-Pen label
-Push button
-Dose selector
-Dose window
-Single Use Needle
-Outer needle cover
-Inner Needle shield
-Needle tip
-Needle
-Foil
You Will Also Need
Figure B
Sharps disposal container
Alcohol wipe

Panel 8

1 Prepare Pen And Needle
Step 1
Wash your hands with soap and water before using YORVIPATH pen. Take your YORVIPATH pen and a needle from the box and check the expiration date on both pen and needle (see Figure C). Do not use if expired.

Figure C

Expiration date OK?
Step 2
Pull off the pen cap and check the inspection window to make sure the medicine inside the pen is clear and colorless (see Figure D).
Important: If the medicine has visible particles in it do not use the pen. Use a new pen.

Figure D

Medicine OK?
Step 3
Pull the foil off the needle (see Figure E). This needle can only be used 1 time.

Figure E

Step 4
Attach the needle straight on to your pen, then screw the needle onto the pen until secure (see Figure F).

Figure F

Step 5

1. Pull off the outer needle cover and
  keep this for later needle removal (see Figure G: a)..
2. Pull off the inner needle shield
  and throw this away (see Figure G: b).

Figure G

Panel 9

2 If New Pen, Test Pen Flow

Day 1
Attention
Only test pen flow (Steps A – C) the first time you use a new pen.
If your pen is already in use, go to section "3 Prepare Injection".

Step A

Turn the dose selector clockwise (to the right) 2 clicks until you see the droplet symbol "" in the dose window (see Figure H).

Note: You can always correct the selection by turning the dose selector.

Figure H

Step B
Make any air bubbles rise to the top of the pen by tapping the inspection window (see Figure I). Keep the pen with the needle tip pointed up.
Note: Tiny air bubbles are ok.

Figure I

tap tap
Step C
Press the push button and watch drops of medicine come out of the needle tip. When you press, make sure that the dose selector rotates back to the symbol "•" (see Figure J).
Important: If you do not see drops of medicine, repeat this test (Steps A – C) up to 5 times. If drops are still not seen, change the needle and repeat the test.

Figure J

Panel 10

3 Prepare Injection and Select Dose
Step 6
Choose injection site. There are two regions of your body you can inject into (see Figure K).
Avoid injecting where skin is red, swollen or scarred. Choose a different injection site each time you inject.

Figure K

Front
Stomach (Abdomen) at least 2 inches away from the belly button
Thighs
Step 7
Wash your hands and clean the injection site with an alcohol wipe (see Figure L).

Figure L

Use alcohol wipe
Step 8
Select your dose as prescribed by your health care provider (15, 18 or 21 mcg) by turning the dose selector clockwise (to the right) (see Figure M).
Important: Make sure not to press the push button while selecting your dose to not spill medicine.
Note: Always throw away your pen and use another pen if you cannot dial a full dose.

Figure M

Panel 11

4 Inject Dose
Attention
Use the injection technique recommended by your health care provider or nurse.
Read this whole section (Steps 9 - 11) before you start to inject.
Step 9
Make sure you can see the dose window.
Insert the needle into the skin (see Figure N).

Figure N

Step 10
Press the push button all the way in and hold steady for 5 seconds.
Make sure the dose selector rotates back to the symbol "●".
This means that you have given the full dose (see Figure O).

Figure O

Pres…
then hold 5 seconds.
Step 11
Slowly remove the pen from the injection site (see Figure P).

Figure P

Panel 12

5 Throw Away Used Needle
Step 12
Reattach the outer needle cover to carefully remove the needle.
Insert the needle tip into the outer needle cover and secure the outer needle cover onto the needle (see Figure Q).
Important: Always reattach the outer needle cover before removing the needle to reduce the risk of needle stick and cross-contamination.

Figure Q

Step 13

Unscrew the needle and throw away the needle safely in accordance with local regulations (see Figure R).

Figure R

Step 14
Click the pen cap firmly onto the pen to protect it between injections and to protect the medicine from light (see Figure S).

Figure S

click!

Panel 13

6 Throw Away Used Pen
Day 14
Important: Always throw away the pen 14 days after first use according to local regulations.
Always throw away your pen and any extra needles after 14 days of use, even if it still has medicine inside (see Figure T). This is important to make sure that you get the full effect of your medicine.

Figure T

This Instructions for Use has been approved by the U.S. Food and Drug Administration.
Approved 10/2025

INSTRUCTIONS FOR USE

Label

Content

FRONT

INSTRUCTIONS FOR USE
Yorvipath®
(palopegteriparatide)
injection, for subcutaneous use
For 24, 27 or 30 mcg doses only
This Instructions for Use contains information on how to inject YORVIPATH
420 mcg/1,4 mL (300 mcg/mL) prefilled pen for 24, 27 or 30 mcg doses only
ascendis pharma

Back

Additional information
If you need help, please ask your health care provider or nurse for advice or contact the Ascendis Pharma Helpline:
Ascendis Pharma Helpline:
Toll-free telephone number:
1-844-442-7236
Ascendis Pharma Bone Diseases A/S
Tuborg Boulevard 12
DK-2900 Hellerup
Denmark
ascendis pharma

Panel 1

Troubleshooting
1. How often must I test the pen flow?
You should only test the pen flow (Section 2) the first time you use a new pen (or if you think it might be damaged) to not waste medicine. The test checks to make sure the medicine flows through the pen so that you get the right doses of medicine.
2. I do not see drops appear after I have tested the pen flow 5 times. What should I do?

If you see no drop on the needle tip after 5 attempts it might be because there is no flow through the pen and needle.

Change the needle (see Section 5, Step 12) and test the pen flow again (see Section 2, Steps A-C). You can be sure the flow works correctly when you see the drop of medicine.

If it still does not work, throw away (discard) the pen and contact your health care provider.
3. How do I know I have completed the injection?
Your injection is only completed after you have pressed the push button all the way in and the dose selector has rotated back to the "∙" and you have kept the needle in the skin for 5 seconds.
4. Why do I have to keep holding the pen in the skin for 5 seconds?
Some medicine might flow back into the pen or flow backward from the injection site and be left on the skin. Holding the pen in the skin for 5 seconds helps to make sure that all the medicine has been injected.
5. I cannot dial the dose selector to the required dose. What should I do?
The pen does not allow a larger dose to be set than what is left in the pen.
If your dose is larger than the amount of medicine left in the pen you will not be able to dial a full dose. You must throw away your pen and take the full dose of medicine with a new pen.

Panel 2

Storing Your Pen

- Until first use, refrigerate your pens between 2°C to 8°C (36°F to 46°F) and keep in the package to protect from light.
- After first use, store your pen for 14 days at room temperature below 30°C (86°F).
- Do not leave your pen in a car or another place where it can get too hot or too cold.
- Do not freeze your pen.
- Store YORVIPATH away from heat.
- Keep the YORVIPATH pen out of the reach of children.

Tip: You should take a new pen out of the refrigerator 20 minutes before first use to allow the medicine to get to room temperature before injecting.

Panel 3

Caring For Your Pen

- Handle your pen with care.
- Keep your pen dry.
- Use a moist cloth to clean your pen.
- Do not drop or knock your pen against hard surfaces. If you do, test the pen flow again (Section 2, Steps A – C) before next use.
- Do not apply extra force to your pen. It might be empty, damaged and no longer works properly.
- Do not attempt to repair a damaged pen yourself. If your pen is damaged, contact the Ascendis Pharma Helpline.

Panel 4

Important Information You Need To Know Before Using Your YORVIPATH Pen
Read and follow this Instructions for Use carefully so that you inject YORVIPATH the right way.
If you do not understand or are unable to complete a step that is described in this Instructions for Use, contact your health care provider or nurse or the Ascendis Pharma Helpline.
Make sure you have received training from your health care provider or nurse before injecting. This is important to make sure that you get the correct treatment.
Inject YORVIPATH into the belly (abdomen) or in the front of the thigh.
Your pen can deliver doses of 24, 27 or 30 mcg. It is used for injections under the skin (subcutaneous) for daily treatment of hypoparathyroidism. Your pen is a prefilled dial-a-dose throw away (disposable) pen.
It contains medicine for 14 days of use and is intended to be used 1 time each day. Do not use more than one injection to achieve the recommended once daily dosage.
You can dial doses of 24, 27 or 30 mcg with the pen.
For Correct Use
If you are blind or visually impaired or if you have lack of concentration do not use your pen without help. Get help from a person who is trained to use the YORVIPATH pen.
Store your pen out of the reach of children and any other persons who do not know how to handle it properly.

Panel 5

- Only use your pen as directed by your health care provider or nurse.
- The pen and needles are for single-patient use only. Do not share your pen or needles with other people. It might lead to infection (cross-contamination).
- Start by checking your pen to make sure it is the correct pen.
- Always check the expiration date on the pen label and needle foil before use.
- Always inspect the pen visually before use to make sure it is not damaged and medicine is clear, colorless and without particles.
- Always use a new needle for each injection.
- Only inject into the abdomen or front of thigh as instructed by your health care provider or nurse. Remember to change injection site for each injection and avoid skin that is red, swollen or scarred.
- Always keep the cap on the pen when it is not in use to protect the medicine from light.
- Remove the needle after every use. Do not store the pen with the needle on.
- Always throw away your pen after 14 days of use, even if it still has medicine left inside. This is important to make sure that you get the right effect of your medicine.
- By failing to follow these instructions you may not get the right dose and may therefore not get the full effect of your medicine.
- Avoid bending or breaking off the pen needle.
- Do not change the injection angle after the needle has been inserted into the skin. Changing the angle can cause the needle to bend or break off. A bent or broken needle can remain stuck in the body or remain completely under the skin. If a broken needle remains stuck in the body or remains under the skin, seek medical help right away.

Panel 6

Compatible Pen Needles
In each of the two inner boxes there are 15 disposable Unifine© Pentips© Needles (31G × 5mm) together with a YORVIPATH prefilled pen for doses of 24, 27 or 30 mcg.
Always use the needles that come with YORVIPATH pen for your injections.
For Correct Disposal
Always put your used YORVIPATH needles in an FDA-cleared sharps disposal container right away after use. Always put your used pen in an FDA-cleared sharps disposal container after 14 days of use.
Do not throw away (dispose of) YORVIPATH in your household trash.
If you do not have an FDA-cleared sharps disposal container, you may use a household container that is:

- made of heavy-duty plastic.
- can be closed with a tight-fitting, puncture resistant lid, without sharps being able to come out.
- upright and stable during use.
- leak-resistant.
- properly labeled to warn of hazardous waste inside the container.

When your sharps disposal container is almost full, you will need to follow your community guidelines for the right way to dispose of your sharps disposal container. For more information about the safe sharps disposal, and for specific information about sharps disposal in the state that you live in, go to the FDA's website at: http://www.fda.gov/safesharpsdisposal. Do not dispose of your used sharps disposal container in your household trash unless your community guidelines permit this. Do not recycle your used sharps disposal container.

Panel 7

Parts Overview
Figure A
Symbols:
-Droplets
-Doses (24, 27 or 30 mcg)
-End-of-dose
-Pen cap
-Inspection window (medicine inside)
-Pen
-Pen label
-Push button
-Dose selector
-Dose window
-Single Use Needle
-Outer needle cover
-Inner Needle shield
-Needle tip
-Needle
-Foil
You Will Also Need Figure B
Sharps disposal container Alcohol wipe

Panel 8

1 Prepare Pen And Needle
Step 1
Wash your hands with soap and water before using YORVIPATH pen. Take your YORVIPATH pen and a needle from the box and check the expiration date on both pen and needle (see Figure C). Do not use if expired.

Figure C

Expiration date OK?
Step 2
Pull off the pen cap and check the inspection window to make sure the medicine inside the pen is clear and colorless (see Figure D).
Important: If the medicine has visible particles in it do not use the pen. Use a new pen.

Figure D

Medicine OK?
Step 3
Pull the foil off the needle (see Figure E). This needle can only be used 1 time.

Figure E

Step 4
Attach the needle straight on to your pen, then screw the needle onto the pen until secure (see Figure F).

Figure F

Step 5

1. Pull off the outer needle cover and
  keep this for later needle removal (see Figure G: a).
2. Pull off the inner needle shield
  and throw this away (see Figure G: b).

Figure G

Panel 9

2 If New Pen, Test Pen Flow

Day 1
Attention
Only test pen flow (Steps A – C) the first time you use a new pen.
If your pen is already in use, go to section "3 Prepare Injection".

Step A

Turn the dose selector clockwise (to the right) 2 clicks until you see the droplet symbol "" in the dose window (see Figure H).

Note: You can always correct the selection by turning the dose selector.

Figure H

Step B
Make any air bubbles rise to the top of the pen by tapping the inspection window (see Figure I). Keep the pen with the needle tip pointed up.
Note: Tiny air bubbles are ok.

Figure I

tap tap
Step C
Press the push button and watch drops of medicine come out of the needle tip. When you press, make sure that the dose selector rotates back to the symbol "•" (see Figure J).
Important: If you do not see drops of medicine, repeat this test (Steps A – C) up to 5 times. If drops are still not seen, change the needle and repeat the test.

Figure J

Panel 10

3 Prepare Injection and Select Dose
Step 6
Choose injection site. There are two regions of your body you can inject into (see Figure K).
Avoid injecting where skin is red, swollen or scarred. Choose a different injection site each time you inject.

Figure K

Front
Stomach (Abdomen) at least 2 inches away from the belly button
Thighs
Step 7
Wash your hands and clean the injection site with an alcohol wipe (see Figure L).

Figure L

Use alcohol wipe
Step 8
Select your dose as prescribed by your health care provider (24, 27 or 30 mcg) by turning the dose selector clockwise (to the right) (see Figure M).
Important: Make sure not to press the push button while selecting your dose to not spill medicine.
Note: Always throw away your pen and use another pen if you cannot dial a full dose.

Figure M

Panel 11

4 Inject Dose
Attention
Use the injection technique recommended by your health care provider or nurse.
Read this whole section (Steps 9 - 11) before you start to inject.
Step 9
Make sure you can see the dose window.
Insert the needle into the skin
(see Figure N).

Figure N

Step 10
Press the push button all the way in and hold steady for 5 seconds. Make sure the dose selector rotates back to the symbol "•". This means that you have given the full dose (see Figure O).

Figure O

Pres…
then hold 5 seconds.
Step 11
Slowly remove the pen from the injection site (see Figure P).

Figure P

Panel 12

5 Throw Away Used Needle

Step 12

Reattach the outer needle cover to carefully remove the needle. Insert the needle tip into the outer needle cover and secure the outer needle cover onto the needle (see Figure Q).

Important: Always reattach the outer needle cover before removing the needle to reduce the risk of needle stick and cross-contamination.
Figure Q
Step 13
Unscrew the needle and throw away the needle safely in accordance with local regulations (see Figure R).
Figure R
Step 14
Click the pen cap firmly onto the pen to protect it between injections and to protect the medicine from light (see Figure S).

Figure S

click!

Panel 13

6 Throw Away Used Pen
Day 14
Important: Always throw away the pen 14 days after first use according to local regulations.
Always throw away your pen and any extra needles after 14 days of use, even if it still has medicine inside (see Figure T). This is important to make sure that you get the full effect of your medicine.

Figure T
This Instructions for Use has been approved by the U.S. Food and Drug Administration.
Approved 10/2025

PRINCIPAL DISPLAY PANEL - 168 mcg/0.56 mL Pen Carton

Yorvipath®
(palopegteriparatide) for injection

168 mcg/0.56 mL prefilled pens

For 6 mcg, 9 mcg or 12 mcg doses only

For subcutaneous use
For single patient use only

Dispense in this sealed carton

Important:

- Follow enclosed Instructions For Use
- Until first use, pens must be refrigerated at
  2°C to 8°C (36°F to 46°F) and keep in the
  package to protect from light
- After first use, store the pen in use at room
  temperature below 30°C (86°F)
- Do not freeze
- Store away from heat
- Every time after use, put pen cap on
  to protect from light
- Throw away the pen in use 14 days after
  first use
- Keep out of the reach of children

Rx Only

PRINCIPAL DISPLAY PANEL - 294 mcg/0.98 mL Pen Carton

Yorvipath®
(palopegteriparatide) for injection

294 mcg/0.98 mL prefilled pens

For 15 mcg, 18 mcg or 21 mcg doses only

For subcutaneous use
For single patient use only

Dispense in this sealed carton

Important:

- Follow enclosed Instructions For Use
- Until first use, pens must be refrigerated at
  2°C to 8°C (36°F to 46°F) and keep in the
  package to protect from light
- After first use, store the pen in use at room
  temperature below 30°C (86°F)
- Do not freeze
- Store away from heat
- Every time after use, put pen cap on
  to protect from light
- Throw away the pen in use 14 days after
  first use
- Keep out of the reach of children

Rx Only

PRINCIPAL DISPLAY PANEL - 420 mcg/1.4 mL Pen Carton

Yorvipath®
(palopegteriparatide) for injection

420 mcg/1.4 mL prefilled pens

For 24 mcg, 27 mcg or 30 mcg doses only

For subcutaneous use
For single patient use only

Dispense in this sealed carton

Important:

- Follow enclosed Instructions For Use
- Until first use, pens must be refrigerated at
  2°C to 8°C (36°F to 46°F) and keep in the
  package to protect from light
- After first use, store the pen in use at room
  temperature below 30°C (86°F)
- Do not freeze
- Store away from heat
- Every time after use, put pen cap on
  to protect from light
- Throw away the pen in use 14 days after
  first use
- Keep out of the reach of children

Rx Only